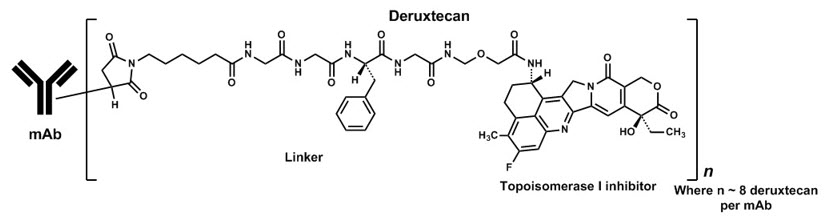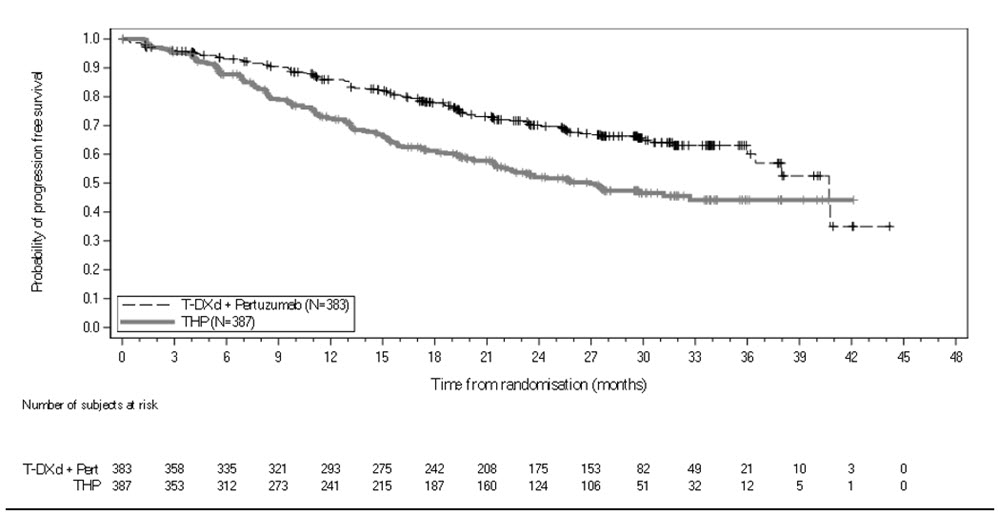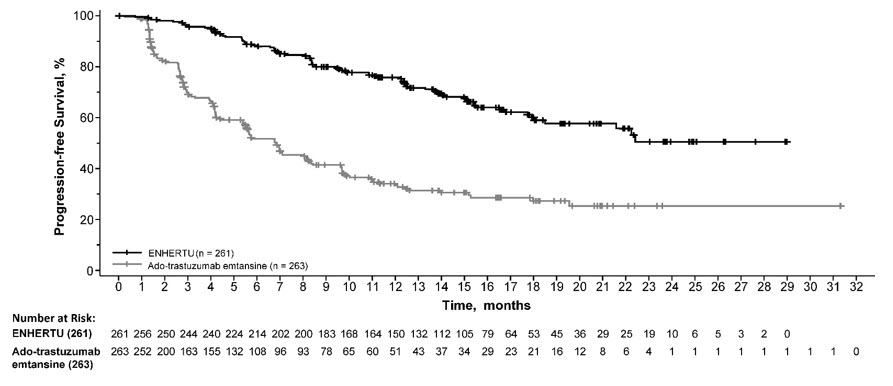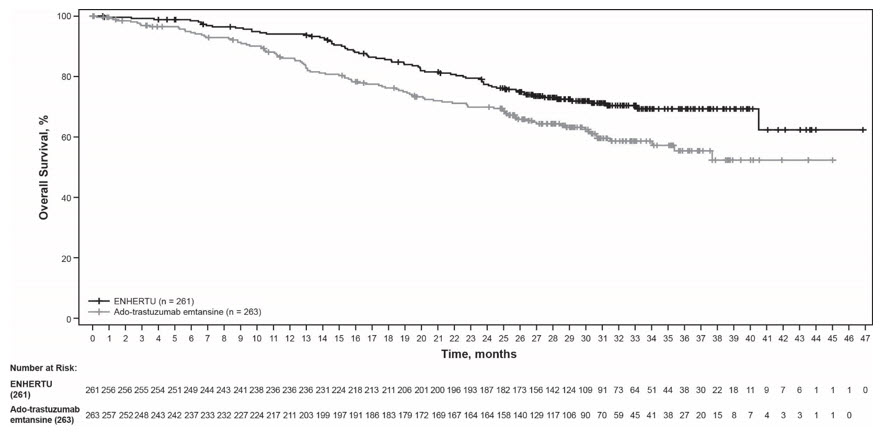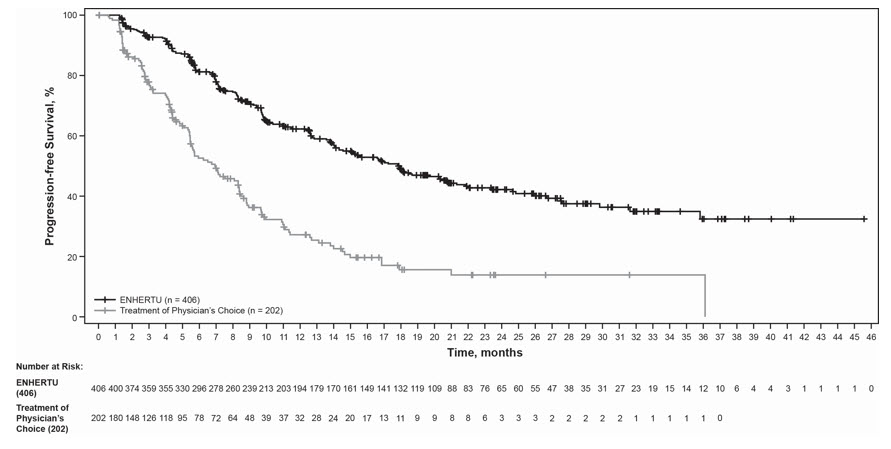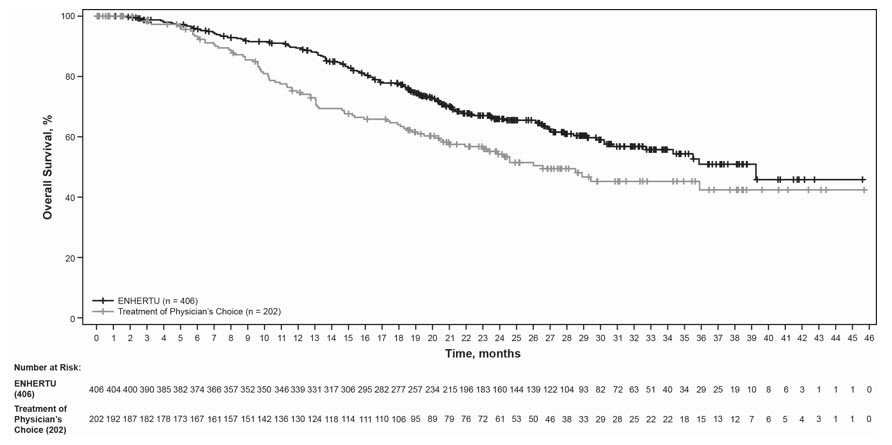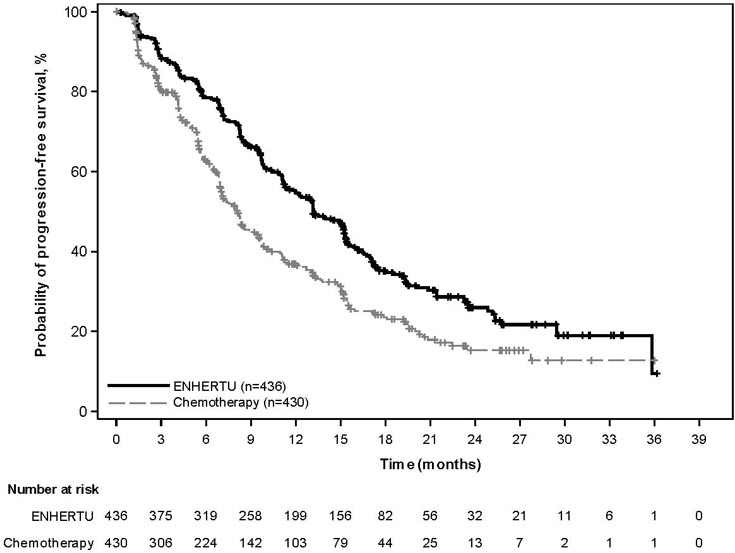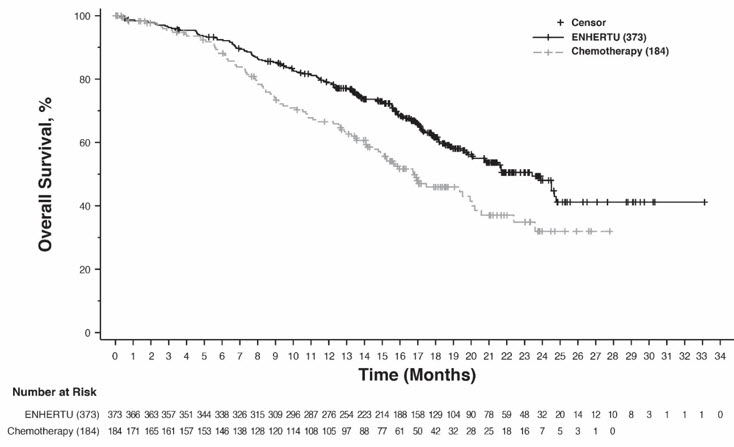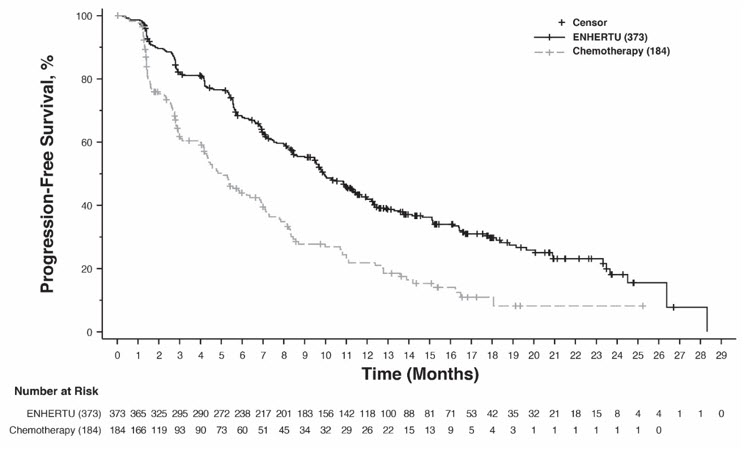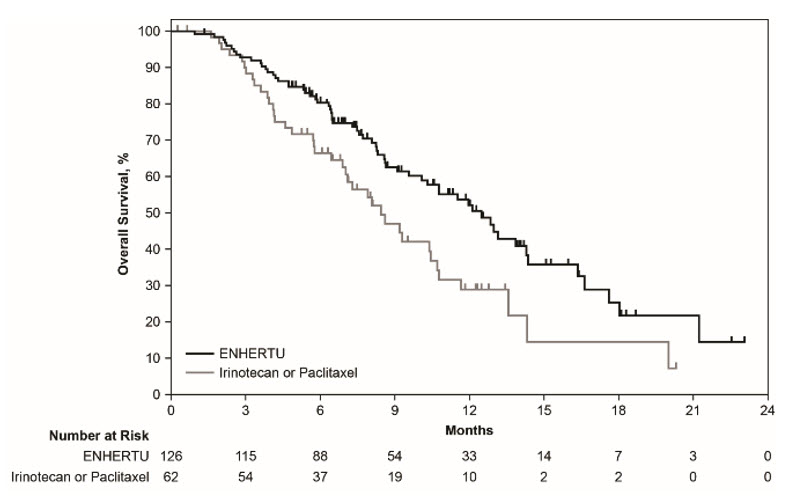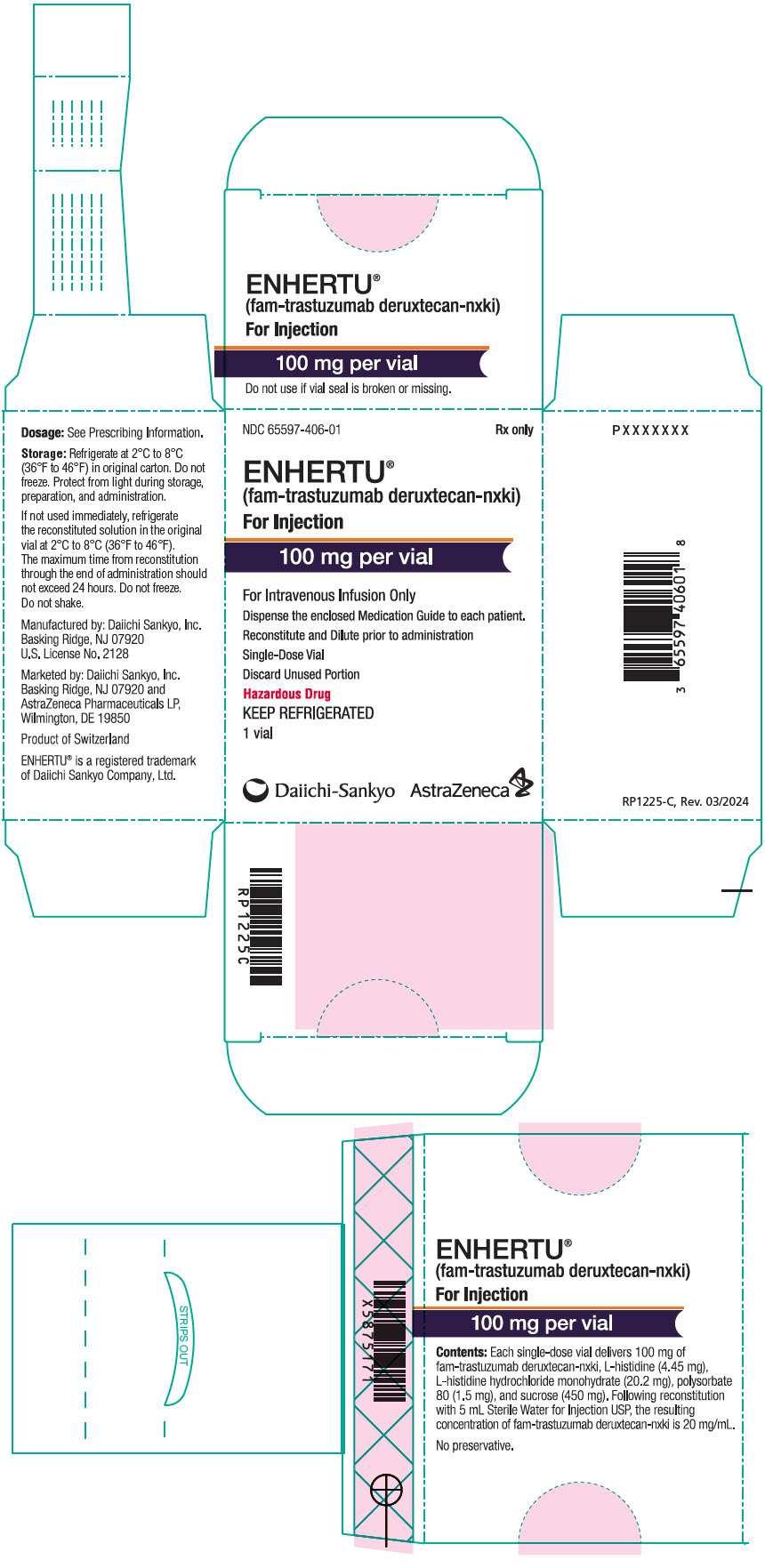 DRUG LABEL: Enhertu
NDC: 65597-406 | Form: INJECTION, POWDER, LYOPHILIZED, FOR SOLUTION
Manufacturer: Daiichi Sankyo Inc.
Category: prescription | Type: HUMAN PRESCRIPTION DRUG LABEL
Date: 20251223

ACTIVE INGREDIENTS: TRASTUZUMAB DERUXTECAN 100 mg/5 mL
INACTIVE INGREDIENTS: HISTIDINE; HISTIDINE HYDROCHLORIDE MONOHYDRATE; SUCROSE; POLYSORBATE 80

HIGHLIGHTS OF PRESCRIBING INFORMATION

These highlights do not include all the information needed to use ENHERTU safely and effectively. See full prescribing information for ENHERTU.
ENHERTU® (fam-trastuzumab deruxtecan-nxki) for injection, for intravenous use
Initial U.S. Approval: 2019

WARNING: INTERSTITIAL LUNG DISEASE and EMBRYO-FETAL TOXICITY

See full prescribing information for complete boxed warning.

- Interstitial lung disease (ILD) and pneumonitis, including fatal cases, have been reported with ENHERTU. Monitor for and promptly investigate signs and symptoms including cough, dyspnea, fever, and other new or worsening respiratory symptoms. Permanently discontinue ENHERTU in all patients with Grade 2 or higher ILD/pneumonitis. Advise patients of the risk and to immediately report symptoms. (2.3, 5.1)
- Exposure to ENHERTU during pregnancy can cause embryo-fetal harm. Advise patients of these risks and the need for effective contraception. (5.4, 8.1, 8.3)

RECENT MAJOR CHANGES

Indications and Usage (1.1) | 12/2025
Indications and Usage (1.2) | 01/2025
Dosage and Administration (2.1, 2.2, 2.3) | 12/2025
Dosage and Administration (2.1, 2.2) | 01/2025
Warnings and Precautions (5.1, 5.2, 5.3) | 12/2025
Warnings and Precautions (5.1, 5.2, 5.3) | 01/2025

1 INDICATIONS AND USAGE

ENHERTU is a HER2-directed antibody and topoisomerase inhibitor conjugate indicated:

HER2-Positive Metastatic Breast Cancer

- in combination with pertuzumab as first-line treatment of adult patients with unresectable or metastatic HER2-positive (IHC 3+ or ISH+) breast cancer, as determined by an FDA-approved test. (1.1)
- as monotherapy for the treatment of adult patients with unresectable or metastatic HER2-positive (IHC 3+ or ISH+) breast cancer who have received a prior anti-HER2-based regimen either in the metastatic setting, or, in the neoadjuvant or adjuvant setting and have developed disease recurrence during or within six months of completing therapy. (1.1)

HER2-Low and HER2-Ultralow Metastatic Breast Cancer

- as monotherapy for the treatment of adult patients with unresectable or metastatic hormone receptor (HR)-positive, HER2-low (IHC 1+ or IHC 2+/ISH-) or HER2-ultralow (IHC 0 with membrane staining) breast cancer, as determined by an FDA-approved test, that has progressed on one or more endocrine therapies in the metastatic setting. (1.2)
- as monotherapy for the treatment of adult patients with unresectable or metastatic HER2-low (IHC 1+ or IHC 2+/ISH-) breast cancer, as determined by an FDA-approved test, who have received a prior chemotherapy in the metastatic setting; or developed disease recurrence during or within 6 months of completing adjuvant chemotherapy. (1.2)

HER2-Mutant Unresectable or Metastatic Non-Small Cell Lung Cancer

- as monotherapy for the treatment of adult patients with unresectable or metastatic non-small cell lung cancer (NSCLC) whose tumors have activating HER2 (ERBB2) mutations, as detected by an FDA-approved test, and who have received a prior systemic therapy* (1.3)

HER2-Positive Locally Advanced or Metastatic Gastric Cancer

- as monotherapy for the treatment of adult patients with locally advanced or metastatic HER2-positive (IHC 3+ or IHC 2+/ISH positive) gastric or gastroesophageal junction adenocarcinoma who have received a prior trastuzumab-based regimen. (1.4)

HER2-Positive (IHC 3+) Unresectable or Metastatic Solid Tumors

- as monotherapy for the treatment of adult patients with unresectable or metastatic HER2-positive (IHC 3+) solid tumors who have received prior systemic treatment and have no satisfactory alternative treatment options* (1.5)

* These indications are approved under accelerated approval based on objective response rate and duration of response. Continued approval for this indication may be contingent upon verification and description of clinical benefit in a confirmatory trial. (14.3, 14.5)

2 DOSAGE AND ADMINISTRATION

- Do not substitute ENHERTU for or with trastuzumab or ado-trastuzumab emtansine. (2.2, 2.4)
- For intravenous infusion only. Do not administer as an intravenous push or bolus. DO NOT use Sodium Chloride Injection, USP. (2.4)
- Premedicate for prevention of chemotherapy-induced nausea and vomiting. (2.2)
- HER2-positive, HER2-low, or HER2-ultralow breast cancer, HER2-mutant NSCLC, and HER2-positive (IHC 3+) solid tumors: ENHERTU 5.4 mg/kg every 3 weeks until disease progression or unacceptable toxicity. (2.2, 2.3)
- HER2-Positive First-line Metastatic Breast Cancer ENHERTU 5.4 mg/kg every 3 weeks (in combination with pertuzumab until disease progression or unacceptable toxicity.
  - Cycle 1, Day 1: ENHERTU 5.4 mg/kg followed by pertuzumab 840 mg. (2.2, 2.3)
  - Subsequent cycles, Day 1: ENHERTU 5.4 mg/kg followed by pertuzumab 420 mg. (2.2, 2.3)
- HER2-positive gastric cancer: 6.4 mg/kg every 3 weeks until disease progression or unacceptable toxicity. (2.2, 2.3)
- Management of adverse reactions (ILD, neutropenia, thrombocytopenia, or left ventricular dysfunction) may require temporary interruption, dose reduction, or discontinuation of ENHERTU. (2.3)

3 DOSAGE FORMS AND STRENGTHS

For injection: 100 mg lyophilized powder in a single-dose vial (3)

4 CONTRAINDICATIONS

None. (4)

5 WARNINGS AND PRECAUTIONS

- Neutropenia: Monitor complete blood counts prior to initiation of ENHERTU and prior to each dose, and as clinically indicated. Manage through treatment interruption or dose reduction. (2.3, 5.2)
- Left Ventricular Dysfunction: Assess left ventricular ejection fraction (LVEF) prior to initiation of ENHERTU and at regular intervals during treatment as clinically indicated. Manage through treatment interruption or discontinuation. Permanently discontinue ENHERTU in patients with symptomatic congestive heart failure (CHF). (2.3, 5.3)

6 ADVERSE REACTIONS

The most common adverse reactions (≥20%), including laboratory abnormalities, in patients with:

- HER2-positive, HER2-low, and HER2-ultralow metastatic breast cancer, HER2-mutant NSCLC, and HER2-positive (including IHC 3+) solid tumors are decreased white blood cell count, nausea, decreased hemoglobin, decreased neutrophil count, decreased lymphocyte count, fatigue, decreased platelet count, increased aspartate aminotransferase, increased alanine aminotransferase, increased blood alkaline phosphatase, vomiting, alopecia, constipation, decreased blood potassium, decreased appetite, diarrhea, and musculoskeletal pain. (6.1)
- HER2-positive metastatic breast cancer in treatment with ENHERTU in combination with pertuzumab are decreased white blood cell count, decreased hemoglobin, decreased neutrophil count, nausea, increased alanine aminotransferase, diarrhea, increased aspartate aminotransferase, decreased lymphocyte count, decreased platelet count, increased blood alkaline phosphatase, decreased blood potassium, fatigue, alopecia, vomiting, upper respiratory tract infection, constipation, decreased appetite, decreased weight, COVID-19, musculoskeletal pain, increased blood bilirubin, and abdominal pain. (6.1)
- HER2-positive gastric cancer are decreased hemoglobin, decreased white blood cell count, decreased neutrophil count, decreased lymphocyte count, decreased platelet count, nausea, decreased appetite, increased aspartate aminotransferase, fatigue, increased blood alkaline phosphatase, increased alanine aminotransferase, diarrhea, decreased blood potassium, vomiting, constipation, increased blood bilirubin, pyrexia, and alopecia. (6.1)

To report SUSPECTED ADVERSE REACTIONS, contact Daiichi Sankyo, Inc. at 1-877-437-7763 or FDA at 1-800-FDA-1088 or www.fda.gov/medwatch.

8 USE IN SPECIFIC POPULATIONS

- Lactation: Advise not to breastfeed. (8.2)
- Females and Males of Reproductive Potential: Verify pregnancy status of females prior to initiation of ENHERTU. (8.3)

FULL PRESCRIBING INFORMATION

WARNING: INTERSTITIAL LUNG DISEASE and EMBRYO-FETAL TOXICITY

- Interstitial Lung Disease (ILD) and pneumonitis, including fatal cases, have been reported with ENHERTU. Monitor for and promptly investigate signs and symptoms including cough, dyspnea, fever, and other new or worsening respiratory symptoms. Permanently discontinue ENHERTU in all patients with Grade 2 or higher ILD/pneumonitis. Advise patients of the risk and the need to immediately report symptoms [see Dosage and Administration (2.3), Warnings and Precautions (5.1)].
- Embryo-Fetal Toxicity: Exposure to ENHERTU during pregnancy can cause embryo-fetal harm. Advise patients of these risks and the need for effective contraception [see Warnings and Precautions (5.4), Use in Specific Populations (8.1, 8.3)].

1 INDICATIONS AND USAGE

1.1 HER2-Positive Metastatic Breast Cancer

- ENHERTU, in combination with pertuzumab, is indicated for the first-line treatment of adult patients with unresectable or metastatic HER2-positive (IHC 3+ or ISH+) breast cancer, as determined by an FDA-approved test [see Dosage and Administration (2.1)].
- ENHERTU, as monotherapy, is indicated for the treatment of adult patients with unresectable or metastatic HER2-positive (IHC 3+ or ISH+) breast cancer who have received a prior anti-HER2-based regimen either in the metastatic setting, or, in the neoadjuvant or adjuvant setting and have developed disease recurrence during or within six months of completing therapy.

1.2 HER2-Low and HER2-Ultralow Metastatic Breast Cancer

ENHERTU, as monotherapy, is indicated for the treatment of adult patients with unresectable or metastatic

- Hormone receptor (HR)-positive HER2-low (IHC 1+ or IHC 2+/ISH-) or HER2-ultralow (IHC 0 with membrane staining) breast cancer, as determined by an FDA-approved test, that has progressed on one or more endocrine therapies in the metastatic setting [see Dosage and Administration (2.1)].
- HER2-low (IHC 1+ or IHC 2+/ISH-) breast cancer, as determined by an FDA-approved test, who have received a prior chemotherapy in the metastatic setting or developed disease recurrence during or within 6 months of completing adjuvant chemotherapy [see Dosage and Administration (2.1)].

1.3 HER2-Mutant Unresectable or Metastatic Non-Small Cell Lung Cancer

ENHERTU, as monotherapy, is indicated for the treatment of adult patients with unresectable or metastatic non-small cell lung cancer (NSCLC) whose tumors have activating HER2 (ERBB2) mutations, as detected by an FDA-approved test, and who have received a prior systemic therapy.

This indication is approved under accelerated approval based on objective response rate and duration of response [see Clinical Studies (14.3)]. Continued approval for this indication may be contingent upon verification and description of clinical benefit in a confirmatory trial.

1.4 HER2-Positive Locally Advanced or Metastatic Gastric Cancer

ENHERTU, as monotherapy, is indicated for the treatment of adult patients with locally advanced or metastatic HER2-positive (IHC 3+ or IHC 2+/ISH positive) gastric or gastroesophageal junction (GEJ) adenocarcinoma who have received a prior trastuzumab-based regimen.

1.5 HER2-Positive (IHC 3+) Unresectable or Metastatic Solid Tumors

ENHERTU, as monotherapy, is indicated for the treatment of adult patients with unresectable or metastatic HER2-positive (IHC 3+) solid tumors who have received prior systemic treatment and have no satisfactory alternative treatment options.

This indication is approved under accelerated approval based on objective response rate and duration of response [see Clinical Studies (14.5)]. Continued approval for this indication may be contingent upon verification and description of clinical benefit in a confirmatory trial.

2 DOSAGE AND ADMINISTRATION

2.1 Patient Selection

HER2-Positive Metastatic Breast Cancer

Select patients for treatment of unresectable or metastatic HER2-positive breast cancer with ENHERTU in combination with pertuzumab based on confirmed HER2-positive status or HER2 gene amplification (IHC 3+ or ISH+) [see Clinical Studies (14.1)].

HER2-Low or HER2-Ultralow Unresectable or Metastatic Breast Cancer

Select patients for treatment of unresectable or metastatic HER2-low (IHC 1+ or IHC 2+/ISH-) or HER2-ultralow (IHC 0 with membrane staining) breast cancer with ENHERTU based on HER2 expression [see Clinical Studies (14.2)].

HER2-Mutant Unresectable or Metastatic NSCLC

Select patients for the treatment of unresectable or metastatic HER2-mutant NSCLC with ENHERTU based on the presence of activating HER2 (ERBB2) mutations in tumor or plasma specimens [see Clinical Studies (14.3)]. If no mutation is detected in a plasma specimen, test tumor tissue.

HER2-Positive Locally Advanced or Metastatic Gastric Cancer

Select patients with locally advanced or metastatic HER2-positive gastric cancer based on HER2 protein overexpression or HER2 gene amplification (IHC 3+ or IHC 2+/ISH+). Reassess HER2 status if it is feasible to obtain a new tumor specimen after prior trastuzumab-based therapy and before treatment with ENHERTU.

HER2-Positive (IHC 3+) Unresectable or Metastatic Solid Tumors

Select patients for treatment of unresectable or metastatic solid tumors with ENHERTU based on HER2-positive (IHC 3+) specimens [see Clinical Studies (14.5)]. An FDA-approved test for the detection of HER2-positive (IHC 3+) solid tumors for treatment with ENHERTU is not currently available.

Additional Patient Selection Information

Information on FDA-approved tests for the detection of HER2 protein expression, HER2 gene amplification, and activating HER2 mutations is available at: http://www.fda.gov/CompanionDiagnostics.

2.2 Recommended Dosage and Schedules

Do not substitute ENHERTU for or with trastuzumab or ado-trastuzumab emtansine.

Slow or interrupt the infusion rate if the patient develops infusion-related symptoms.

Permanently discontinue ENHERTU in case of severe infusion reactions.

Premedication

ENHERTU is highly emetogenic [see Adverse Reactions (6.1)], which includes delayed nausea and/or vomiting. Administer prophylactic antiemetic medications per local institutional guidelines for prevention of chemotherapy-induced nausea and vomiting.

The recommended dosages for ENHERTU as monotherapy and ENHERTU in combination with pertuzumab are presented in Table 1. Administer ENHERTU as an intravenous infusion [see Dosage and Administration (2.4)].

Table 1: Recommended Dosage
Indication | Recommended ENHERTU Dosage | Duration of Therapy
HER2-Positive, HER2-Low, or HER2-Ultralow Metastatic Breast Cancer, HER2-Mutant Unresectable or Metastatic NSCLC, and HER2-Positive (IHC 3+) Unresectable or Metastatic Solid Tumors as monotherapy | ENHERTU 5.4 mg/kg every 3 weeks | Until disease progression or unacceptable toxicity
HER2-Positive Metastatic Breast Cancer in combination with pertuzumab | Cycle 1, Day 1: ENHERTU 5.4 mg/kg, followed by pertuzumab 840 mg [Administer pertuzumab 30 minutes after ENHERTU.] Subsequent cycles, Day 1: ENHERTU 5.4 mg/kg, followed by pertuzumab 420 mg every 3 weeks | Until disease progression or unacceptable toxicity
HER2-Positive Locally Advanced or Metastatic Gastric Cancer as monotherapy | ENHERTU 6.4 mg/kg every 3 weeks | Until disease progression or unacceptable toxicity

2.3 Dosage Modifications

Management of adverse reactions may require temporary interruption, dose reduction, or treatment discontinuation of ENHERTU as described in Tables 2 and 3. Refer to the Prescribing Information for pertuzumab for dose modification recommendations. Pertuzumab is not to be administered as a single agent.

Do not re-escalate the ENHERTU dose after a dose reduction is made.

If a planned dose is delayed or missed, administer as soon as possible; do not wait until the next planned cycle. Adjust the schedule of administration to maintain a 3-week interval between doses. Administer the infusion at the dose and rate the patient tolerated in the most recent infusion.

Table 2: Dosage Reduction Schedule
Dose Reduction Schedule | Breast Cancer, NSCLC, and IHC 3+ Solid Tumors | Gastric Cancer
Recommended starting dose | 5.4 mg/kg | 6.4 mg/kg
First dose reduction | 4.4 mg/kg | 5.4 mg/kg
Second dose reduction | 3.2 mg/kg | 4.4 mg/kg
Requirement for further dose reduction | Discontinue treatment. | Discontinue treatment.

Table 3: Dosage Modifications for Adverse Reactions
Adverse Reaction | Severity |  | Treatment Modification
Interstitial Lung Disease (ILD)/ Pneumonitis [see Warnings and Precautions (5.1)] | Asymptomatic ILD/pneumonitis (Grade 1) |  | Interrupt ENHERTU until resolved to Grade 0, then:; - if resolved in 28 days or less from date of onset, maintain dose. - if resolved in greater than 28 days from date of onset, reduce dose one level (see Table 1). - consider corticosteroid treatment as soon as ILD/pneumonitis is suspected.
Interstitial Lung Disease (ILD)/ Pneumonitis [see Warnings and Precautions (5.1)] | Symptomatic ILD/pneumonitis (Grade 2 or greater) |  | - Permanently discontinue ENHERTU. - Promptly initiate corticosteroid treatment as soon as ILD/pneumonitis is suspected.
Neutropenia [see Warnings and Precautions (5.2)] | Grade 3 (less than 1.0 to 0.5 × 10^9/L) |  | - Interrupt ENHERTU until resolved to Grade 2 or less, then maintain dose.
Neutropenia [see Warnings and Precautions (5.2)] | Grade 4 (less than 0.5 × 10^9/L) |  | - Interrupt ENHERTU until resolved to Grade 2 or less. - Reduce dose by one level (see Table 1).
Febrile Neutropenia [see Warnings and Precautions (5.2)] | Absolute neutrophil count of less than 1.0 × 10^9/L and temperature greater than 38.3°C or a sustained temperature of 38°C or greater for more than one hour |  | - Interrupt ENHERTU until resolved. - Reduce dose by one level (see Table 1).
Thrombocytopenia [see Adverse Reactions (6.1)] | Grade 3 (platelets less than 50 to 25 × 10^9/L) |  | - Interrupt ENHERTU until resolved to Grade 1 or less, then maintain dose.
Thrombocytopenia [see Adverse Reactions (6.1)] | Grade 4 (platelets less than 25 × 10^9/L) |  | - Interrupt ENHERTU until resolved to Grade 1 or less. - Reduce dose by one level (see Table 1).
Left Ventricular Dysfunction [see Warnings and Precautions (5.3)] | LVEF greater than 45% and absolute decrease from baseline is 10% to 20% |  | - Continue treatment with ENHERTU.
Left Ventricular Dysfunction [see Warnings and Precautions (5.3)] | LVEF 40% to 45% | And absolute decrease from baseline is less than 10% | - Continue treatment with ENHERTU. - Repeat LVEF assessment within 3 weeks.
Left Ventricular Dysfunction [see Warnings and Precautions (5.3)] | LVEF 40% to 45% | And absolute decrease from baseline is 10% to 20% | - Interrupt ENHERTU. - Repeat LVEF assessment within 3 weeks. - If LVEF has not recovered to within 10% from baseline, permanently discontinue ENHERTU. - If LVEF recovers to within 10% from baseline, resume treatment with ENHERTU at the same dose.
Left Ventricular Dysfunction [see Warnings and Precautions (5.3)] | LVEF less than 40% or absolute decrease from baseline is greater than 20% |  | - Interrupt ENHERTU. - Repeat LVEF assessment within 3 weeks. - If LVEF of less than 40% or absolute decrease from baseline of greater than 20% is confirmed, permanently discontinue ENHERTU.
Left Ventricular Dysfunction [see Warnings and Precautions (5.3)] | Symptomatic congestive heart failure (CHF) |  | - Permanently discontinue ENHERTU.
Toxicity grades are in accordance with National Cancer Institute Common Terminology Criteria for Adverse Events Version 5.0 (NCI CTCAE v.5.0).

2.4 Preparation and Administration

In order to prevent medication errors, check the vial labels to ensure that the drug being prepared and administered is ENHERTU (fam-trastuzumab deruxtecan-nxki) and not trastuzumab or ado-trastuzumab emtansine.

Reconstitute and further dilute ENHERTU prior to intravenous infusion. Use appropriate aseptic technique.

ENHERTU (fam-trastuzumab deruxtecan-nxki) is a hazardous drug. Follow applicable special handling and disposal procedures.^1

Reconstitution

- Reconstitute immediately before dilution.
- More than one vial may be needed for a full dose. Calculate the dose (mg), the total volume of reconstituted ENHERTU solution required, and the number of vial(s) of ENHERTU needed [see Dosage and Administration (2.2)].
- Reconstitute each 100 mg vial by using a sterile syringe to slowly inject 5 mL of Sterile Water for Injection, USP into each vial to obtain a final concentration of 20 mg/mL.
- Swirl the vial gently until completely dissolved. Do not shake.
- If not used immediately, store the reconstituted ENHERTU vials in a refrigerator at 2ºC to 8ºC (36ºF to 46ºF) for up to 24 hours from the time of reconstitution, protect the vial from light. Do not freeze.
- The product does not contain a preservative. Discard unused ENHERTU after 24 hours refrigerated.

Dilution

- Withdraw the calculated amount from the vial(s) using a sterile syringe. Parenteral drug products should be inspected visually for particulate matter and discoloration prior to administration whenever solution and container permit. The solution should be clear and colorless to light yellow. Do not use if visible particles are observed or if the solution is cloudy or discolored.
- Dilute the calculated volume of reconstituted ENHERTU in an intravenous infusion bag containing 100 mL of 5% Dextrose Injection, USP. DO NOT use Sodium Chloride Injection, USP. ENHERTU is compatible with an infusion bag made of polyvinylchloride or polyolefin (copolymer of ethylene and polypropylene).
- Gently invert the infusion bag to thoroughly mix the solution. Do not shake.
- Cover the infusion bag to protect from light.
- Discard any unused portion left in the vials.

Administration

- If not used immediately, store the diluted ENHERTU in a refrigerator at 2ºC to 8ºC (36ºF to 46ºF) for up to 24 hours or at room temperature between 20ºC to 25ºC (68ºF to 77 ºF) for up to 4 hours including preparation and infusion time.
- Protect from light. Do not freeze.
- The maximum time from reconstitution of the vial through the end of administration should not exceed 24 hours.
- If the prepared infusion solution was stored refrigerated (2ºC to 8ºC [36ºF to 46ºF]), allow the solution to reach room temperature prior to administration. Cover the infusion bag to protect from light.
- Administer ENHERTU as an intravenous infusion only with an infusion set made of polyolefin or polybutadiene.
- Administer ENHERTU with a 0.20 or 0.22 micron in-line polyethersulfone (PES) or polysulfone (PS) filter.
- Do NOT administer as an intravenous push or bolus.
- Cover the infusion bag to protect from light during administration.
- Do not mix ENHERTU with other drugs or administer other drugs through the same intravenous line.
- First infusion: Administer infusion over 90 minutes.
- Subsequent infusions: Administer over 30 minutes if prior infusions were well tolerated.

3 DOSAGE FORMS AND STRENGTHS

For injection: 100 mg of fam-trastuzumab deruxtecan-nxki as a white to yellowish white lyophilized powder in a single-dose vial for reconstitution and further dilution

4 CONTRAINDICATIONS

None.

5 WARNINGS AND PRECAUTIONS

5.1 Interstitial Lung Disease/Pneumonitis

Severe, life-threatening, or fatal interstitial lung disease (ILD), including pneumonitis, can occur in patients treated with ENHERTU monotherapy or ENHERTU in combination with pertuzumab [see Adverse Reactions (6.1)]. A higher incidence of Grade 1 and 2 ILD/pneumonitis has been observed in patients with moderate renal impairment.

Advise patients to immediately report cough, dyspnea, fever, and/or any new or worsening respiratory symptoms. Monitor patients for signs and symptoms of ILD. Promptly investigate evidence of ILD. Evaluate patients with suspected ILD by radiographic imaging. Consider consultation with a pulmonologist. For asymptomatic (Grade 1) ILD, consider corticosteroid treatment (e.g., ≥0.5 mg/kg/day prednisolone or equivalent). Withhold ENHERTU until recovery [see Dosage and Administration (2.3)]. In cases of symptomatic ILD (Grade 2 or greater), promptly initiate systemic corticosteroid treatment (e.g., ≥1 mg/kg/day prednisolone or equivalent) and continue for at least 14 days followed by gradual taper for at least 4 weeks. Permanently discontinue ENHERTU in patients who are diagnosed with symptomatic (Grade 2 or greater) ILD [see Dosage and Administration (2.3)].

HER2-Positive, HER2-Low, and HER2-Ultralow Metastatic Breast Cancer, HER2-Mutant NSCLC, and Solid Tumors (Including IHC 3+) (5.4 mg/kg)

ENHERTU as Monotherapy

In patients treated with ENHERTU 5.4 mg/kg, ILD occurred in 12% of patients. Median time to first onset was 5.5 months (range: 0.9 to 31.5). Fatal outcomes due to ILD and/or pneumonitis occurred in 0.9% of patients treated with ENHERTU.

ENHERTU in Combination with Pertuzumab

In patients treated with ENHERTU 5.4 mg/kg in combination with pertuzumab (N=431), ILD occurred in 12% of patients. Median time to first onset was 8.0 months (range: 0.6 to 33.8). Fatal outcomes due to ILD and/or pneumonitis occurred in 0.5% of patients treated with ENHERTU in combination with pertuzumab.

HER2-Positive Locally Advanced or Metastatic Gastric Cancer (6.4 mg/kg)

In patients with locally advanced or metastatic HER2-positive gastric or GEJ adenocarcinoma treated with ENHERTU 6.4 mg/kg, ILD occurred in 10% of patients. Median time to first onset was 2.8 months (range: 1.2 to 21).

5.2 Neutropenia

Severe neutropenia, including febrile neutropenia, can occur in patients treated with ENHERTU monotherapy or ENHERTU in combination with pertuzumab.

Monitor complete blood counts prior to initiation of ENHERTU and prior to each dose, and as clinically indicated. Based on the severity of neutropenia, ENHERTU may require dose interruption or reduction [see Dosage and Administration (2.3)].

HER2-Positive, HER2-Low, and HER2-Ultralow Metastatic Breast Cancer, HER2-Mutant NSCLC, and Solid Tumors (Including IHC 3+) (5.4 mg/kg)

ENHERTU as Monotherapy

In patients treated with ENHERTU 5.4 mg/kg, a decrease in neutrophil count was reported in 65% of patients. Nineteen percent had Grade 3 or 4 decreased neutrophil count. Median time to first onset of decreased neutrophil count was 22 days (range: 2 to 939). Febrile neutropenia was reported in 1.2% of patients.

ENHERTU in Combination with Pertuzumab

In patients treated with ENHERTU 5.4 mg/kg in combination with pertuzumab (N=431), decreased neutrophil count occurred in 79% of patients. Median time to first onset was 22 days (range: 5 to 994). Twenty-nine percent had Grades 3 or 4 decreased neutrophil count. Febrile neutropenia was reported in 2.6% of patients.

HER2-Positive Locally Advanced or Metastatic Gastric Cancer (6.4 mg/kg)

In patients with locally advanced or metastatic HER2-positive gastric or GEJ adenocarcinoma treated with ENHERTU 6.4 mg/kg, a decrease in neutrophil count was reported in 72% of patients. Fifty-one percent had Grade 3 or 4 decreased neutrophil count. Median time to first onset of decreased neutrophil count was 16 days (range: 4 to 187). Febrile neutropenia was reported in 4.8% of patients.

5.3 Left Ventricular Dysfunction

Patients treated with ENHERTU may be at increased risk of developing left ventricular dysfunction. Left ventricular ejection fraction (LVEF) decrease has been observed with anti-HER2 therapies, including ENHERTU.

Assess LVEF prior to initiation of ENHERTU and at regular intervals during treatment as clinically indicated. Manage LVEF decrease through treatment interruption. Permanently discontinue ENHERTU if LVEF of less than 40% or absolute decrease from baseline of greater than 20% is confirmed. Permanently discontinue ENHERTU in patients with symptomatic congestive heart failure (CHF) [see Dosage and Administration (2.3)].

Treatment with ENHERTU has not been studied in patients with a history of clinically significant cardiac disease or LVEF less than 50% prior to initiation of treatment.

HER2-Positive, HER2-Low, and HER2-Ultralow Metastatic Breast Cancer, HER2-Mutant NSCLC, and Solid Tumors (Including IHC 3+) (5.4 mg/kg)

ENHERTU as Monotherapy

In patients treated with ENHERTU 5.4 mg/kg, LVEF decrease was reported in 4.6% of patients, of which 0.6% were Grade 3 or 4.

ENHERTU in Combination with Pertuzumab

In patients treated with ENHERTU 5.4 mg/kg in combination with pertuzumab (N=431), LVEF decrease was reported in 11% of patients, of which 2.1% were Grade 3 or 4.

HER2-Positive Locally Advanced or Metastatic Gastric Cancer (6.4 mg/kg)

In patients with locally advanced or metastatic HER2-positive gastric or GEJ adenocarcinoma treated with ENHERTU 6.4 mg/kg, no clinical adverse events of heart failure were reported; however, on echocardiography, 8% were found to have asymptomatic Grade 2 decrease in LVEF.

5.4 Embryo-Fetal Toxicity

Based on its mechanism of action, ENHERTU can cause fetal harm when administered to a pregnant woman. In postmarketing reports, use of a HER2-directed antibody during pregnancy resulted in cases of oligohydramnios manifesting as fatal pulmonary hypoplasia, skeletal abnormalities, and neonatal death. Based on its mechanism of action, the topoisomerase inhibitor component of ENHERTU, DXd, can also cause embryo-fetal harm when administered to a pregnant woman because it is genotoxic and targets actively dividing cells [see Use in Specific Populations (8.1), Clinical Pharmacology (12.1), Nonclinical Toxicology (13.1)]. Advise patients of the potential risks to a fetus.

Verify the pregnancy status of females of reproductive potential prior to the initiation of ENHERTU. Advise females of reproductive potential to use effective contraception during treatment and for 7 months after the last dose of ENHERTU. Advise male patients with female partners of reproductive potential to use effective contraception during treatment with ENHERTU and for 4 months after the last dose of ENHERTU [see Use in Specific Populations (8.1, 8.3)].

6 ADVERSE REACTIONS

The following clinically significant adverse reactions are described elsewhere in the labeling:

- Interstitial Lung Disease/Pneumonitis [see Warnings and Precautions (5.1)]
- Neutropenia [see Warnings and Precautions (5.2)]
- Left Ventricular Dysfunction [see Warnings and Precautions (5.3)]

6.1 Clinical Trials Experience

Because clinical trials are conducted under widely varying conditions, adverse reaction rates observed in the clinical trials of a drug cannot be directly compared to rates in the clinical trials of another drug and may not reflect the rates observed in practice.

HER2-Positive, HER2-Low, and HER2-Ultralow Metastatic Breast Cancer, HER2-Mutant NSCLC, and Solid Tumors (Including IHC 3+) (5.4 mg/kg)

The pooled safety population described in WARNINGS and PRECAUTIONS reflects exposure to ENHERTU 5.4 mg/kg intravenously every 3 weeks in 2233 patients in Study DS8201-A-J101 (NCT02564900), DESTINY-Breast01, DESTINY- Breast02, DESTINY-Breast03, DESTINY-Breast04, DESTINY-Breast06, DESTINY-Lung01, DESTINY-Lung02, DESTINY-CRC02, and DESTINY-PanTumor02. Among these patients, 67% were exposed for greater than 6 months and 38% were exposed for greater than 12 months. In this pooled safety population, the most common (≥20%) adverse reactions (including laboratory abnormalities) were decreased white blood cell count (73%), nausea (72%), decreased hemoglobin (67%), decreased neutrophil count (65%), decreased lymphocyte count (60%), fatigue (55%), decreased platelet count (48%), increased aspartate aminotransferase (46%), increased alanine aminotransferase (44%), increased blood alkaline phosphatase (39%), vomiting (38%), alopecia (37%), constipation (32%), decreased blood potassium (32%), decreased appetite (31%), diarrhea (30%), and musculoskeletal pain (24%).

ENHERTU in Combination with Pertuzumab

The pooled safety population described in WARNINGS and PRECAUTIONS reflects exposure to ENHERTU 5.4 mg/kg in combination with pertuzumab intravenously every 3 weeks in 431 patients in DESTINY-Breast07 (n=50), and DESTINY-Breast09 (n=381). Among these patients, 86% were exposed for greater than 6 months and 73% were exposed for greater than 12 months. In this pooled safety population, the most common (≥20%) adverse reactions (including laboratory abnormalities) were decreased white blood cell count (86%), decreased hemoglobin (80%), decreased neutrophil count (79%), nausea (74%), increased alanine aminotransferase (65%), diarrhea (64%), increased aspartate aminotransferase (63%), decreased lymphocyte count (61%), decreased platelet count (55%), increased blood alkaline phosphatase (54%), decreased blood potassium (54%), fatigue (53%), alopecia (48%), vomiting (46%), upper respiratory tract infection (32%), constipation (31%), decreased appetite (31%), decreased weight (28%), musculoskeletal pain (23%), increased blood bilirubin (23%), and abdominal pain (22%).

HER2-Positive Locally Advanced or Metastatic Gastric Cancer (6.4 mg/kg)

The data described in WARNINGS and PRECAUTIONS reflect exposure to ENHERTU 6.4 mg/kg intravenously every 3 weeks in 125 patients in DESTINY-Gastric01.

HER2-Positive Metastatic Breast Cancer

DESTINY-Breast09

The safety of ENHERTU 5.4 mg/kg in combination with pertuzumab was evaluated in DESTINY-Breast09, a randomized, three-arm, multicenter study including 763 patients with HER2-positive (IHC 3+ or ISH+) unresectable or metastatic breast cancer [see Clinical Studies (14.1)]. Three hundred eighty-one patients received ENHERTU in combination with pertuzumab and 382 patients received THP (taxane [docetaxel or paclitaxel], trastuzumab, and pertuzumab). Among patients who received ENHERTU in combination with pertuzumab, the median duration of treatment was 22 months (range: 0.3 months to 44.5 months).

Serious adverse reactions occurred in 27% of patients receiving ENHERTU in combination with pertuzumab. Serious adverse reactions in >1% of patients were diarrhea, pneumonia, febrile neutropenia, hypokalemia, vomiting, ILD, pulmonary embolism, and sepsis.

Fatalities due to adverse reactions occurred in 3.4% of patients including pneumonia (n=3), ILD (n=2), sepsis (n=2), pulmonary embolism, septic shock, acute kidney injury, dyspnea, febrile neutropenia, and intestinal ischemia (one patient each). ENHERTU was discontinued for adverse reactions in 21% of patients. The most frequent adverse reactions (>2%) associated with permanent discontinuation was ILD/pneumonitis (6.6%).

Dose interruptions due to adverse reactions occurred in 69% of patients. The most frequent adverse reactions (>2%) associated with dose interruption were COVID-19, neutropenia, upper respiratory tract infection, fatigue, anemia, hypokalemia, ILD/pneumonitis, thrombocytopenia, pneumonia, diarrhea, transaminase increased, leukopenia, cough, pyrexia, decreased appetite, and blood bilirubin increased.

Dose reductions occurred in 46% of patients treated with ENHERTU in combination with pertuzumab. The most frequent adverse reactions (>2%) associated with dose reduction were fatigue, neutropenia, nausea, diarrhea, ILD/pneumonitis, thrombocytopenia, vomiting, transaminases increased, decreased weight, febrile neutropenia, and hypokalemia.

The most common (≥20%) adverse reactions, including laboratory abnormalities, were decreased white blood cell count, decreased hemoglobin, decreased neutrophil count, nausea, increased alanine aminotransferase, diarrhea, increased aspartate aminotransferase decreased lymphocyte count, decreased platelet count, increased blood alkaline phosphatase, decreased blood potassium, fatigue, alopecia, vomiting, upper respiratory tract infection, constipation, decreased appetite, decreased weight, COVID-19, musculoskeletal pain, increased blood bilirubin, and abdominal pain.

Tables 4 and 5 summarize common adverse reactions and laboratory abnormalities observed in DESTINY-Breast09.

Table 4: Common Adverse Reactions (≥10% All Grades or ≥2% Grades 3 or 4) in Patients Treated with ENHERTU in Combination with Pertuzumab in DESTINY-Breast09
Adverse Reactions | ENHERTU 5.4 mg/kg + Pertuzumab N= 381 |  | THP [THP=taxane [docetaxel or paclitaxel], trastuzumab, and pertuzumab] N=382
 | All Grades % | Grade 3-4 % | All Grades % | Grades 3-4 %
Gastrointestinal Disorders
Nausea | 75 | 5 | 34 | 0.3
Diarrhea | 64 | 8 | 62 | 6
Vomiting | 46 | 2.4 | 18 | 0.5
Constipation | 33 | 0.3 | 12 | 0
Abdominal pain [including abdominal discomfort, abdominal pain, abdominal pain lower, abdominal pain upper, gastrointestinal pain.] | 23 | 0.3 | 13 | 0
Stomatitis [including aphthous ulcer, mouth ulceration, oral mucosal eruption, stomatitis] | 16 | 1.3 | 17 | 1.3
Dyspepsia | 12 | 0 | 6 | 0
General Disorders and Administration Site Conditions
Fatigue [including asthenia, fatigue, lethargy, malaise.] | 53 | 8 | 42 | 2.1
Pyrexia | 16 | 0 | 18 | 1.0
Skin and Subcutaneous Tissue Disorders
Alopecia | 48 | 0 | 53 | 0.5
Rash [including rash, rash macular, rash maculo-papular, rash pruritic, rash pustular.] | 17 | 0.3 | 22 | 0.3
Pruritus | 11 | 0 | 11 | 0.3
Infections and Infestations
Upper respiratory tract infection [including Influenza, Influenza like illness, laryngitis, nasopharyngitis, pharyngitis, rhinitis, sinusitis, upper respiratory tract infection.] | 33 | 1.6 | 30 | 0.5
COVID-19 | 28 | 0.3 | 22 | 0.3
Metabolism and Nutrition Disorders
Decreased appetite | 32 | 2.4 | 18 | 0.8
Hypoalbuminemia | 11 | 0.3 | 8 | 0.3
Investigations
Decreased weight | 30 | 3.1 | 11 | 0.8
Musculoskeletal and Connective Tissue Disorders
Musculoskeletal pain [including back pain, bone pain, muscle spasms, musculoskeletal chest pain, musculoskeletal pain, myalgia, neck pain, pain in extremity.] | 24 | 1 | 33 | 0.3
Nervous System Disorders
Headache [including headache, migraine.] | 19 | 0.3 | 14 | 0
Dysgeusia | 13 | 0 | 9 | 0
Dizziness | 12 | 0.3 | 10 | 0
Respiratory, Thoracic, and Mediastinal Disorders
Cough | 17 | 0.3 | 13 | 0
Interstitial lung disease [Interstitial lung disease (grouped term) includes PTs of chronic obstructive pulmonary disease (n=1), interstitial lung disease (n=23), pneumonia (n=3), pneumonitis (n=22). These events were adjudicated as ILD and related to use of T-DXd] | 12 | 0 | 1 | 0
Eye Disorders
Dry eye | 11 | 0 | 6 | 0

Other clinically relevant adverse reactions reported in less than 10% of patients treated with ENHERTU in combination with pertuzumab were:

- Blood and Lymphatic System Disorders: febrile neutropenia (2.9%)
- Eye Disorders: blurred vision (4.2%)
- Gastrointestinal Disorders: abdominal distension (6%), gastritis (3.9%), flatulence (2.4%)
- Injury, poisoning, and procedural complications: infusion related reaction (1.8%) [including hypersensitivity and infusion-related reactions
- Investigations: increased blood bilirubin (9%), increased blood creatinine (3.1%)
- Metabolism and Nutrition Disorders: dehydration (2.9%)
- Respiratory, Thoracic, and Mediastinal Disorders: epistaxis (8%), dyspnea (6%)
- Skin and Subcutaneous Tissue Disorders: skin hyperpigmentation (6%) [including skin hyperpigmentation, skin discoloration, and pigmentation disorder]

Table 5: Selected Laboratory Abnormalities in Patients in DESTINY-Breast09
Laboratory Parameter | ENHERTU 5.4 mg/kg + Pertuzumab N= 381 |  | THP [THP=taxane [docetaxel or paclitaxel], trastuzumab, and pertuzumab]] N=382
Laboratory Parameter | All Grades % | Grade 3-4 % | All Grades % | Grades 3-4 %
Hematology
Decreased white blood cell count | 87 | 11 | 82 | 31
Decreased hemoglobin | 80 | 12 | 86 | 6
Decreased neutrophil count | 78 | 29 | 66 | 40
Decreased lymphocyte count | 62 | 14 | 58 | 11
Decreased platelet count | 56 | 8 | 20 | 1.9
Chemistry
Increased alanine aminotransferase | 66 | 3.2 | 45 | 1.9
Increased aspartate aminotransferase | 62 | 2.1 | 41 | 1.9
Increased blood alkaline phosphatase | 55 | 0.3 | 36 | 0.3
Decreased blood potassium | 54 | 20 | 29 | 6
Increased blood bilirubin | 23 | 0.3 | 10 | 0.3
Increased blood creatinine | 9 | 1.8 | 7 | 0.3
Percentages were calculated using patients with worsening laboratory values from baseline and the number of patients with both baseline and post-treatment measurements as the denominator.
Frequencies were based on NCI CTCAE v.5.0 grade-derived laboratory abnormalities.

DESTINY-Breast03

The safety of ENHERTU was evaluated in 257 patients with unresectable or metastatic HER2-positive breast cancer who received at least one dose of ENHERTU 5.4 mg/kg in DESTINY-Breast03 [see Clinical Studies (14.1)]. ENHERTU was administered by intravenous infusion once every three weeks. The median duration of treatment was 14 months (range: 0.7 to 30) for patients who received ENHERTU and 7 months (range: 0.7 to 25) for patients who received ado-trastuzumab emtansine.

Serious adverse reactions occurred in 19% of patients receiving ENHERTU. Serious adverse reactions in >1% of patients who received ENHERTU were vomiting, interstitial lung disease, pneumonia, pyrexia, and urinary tract infection. Fatalities due to adverse reactions occurred in 0.8% of patients including COVID-19 and sudden death (one patient each).

ENHERTU was permanently discontinued in 14% of patients, of which ILD/pneumonitis accounted for 8%. Dose interruptions due to adverse reactions occurred in 44% of patients treated with ENHERTU. The most frequent adverse reactions (>2%) associated with dose interruption were neutropenia, leukopenia, anemia, thrombocytopenia, pneumonia, nausea, fatigue, and ILD/pneumonitis. Dose reductions occurred in 21% of patients treated with ENHERTU. The most frequent adverse reactions (>2%) associated with dose reduction were nausea, neutropenia, and fatigue.

The most common (≥20%) adverse reactions, including laboratory abnormalities, were nausea, decreased white blood cell count, decreased neutrophil count, increased aspartate aminotransferase, decreased hemoglobin, decreased lymphocyte count, increased alanine aminotransferase, decreased platelet count, fatigue, vomiting, increased blood alkaline phosphatase, alopecia, decreased blood potassium, constipation, musculoskeletal pain, diarrhea, decreased appetite, headache, respiratory infection, abdominal pain, increased blood bilirubin, and stomatitis.

Tables 6 and 7 summarize common adverse reactions and laboratory abnormalities observed in DESTINY-Breast03.

Table 6: Common Adverse Reactions (≥10% All Grades or ≥2% Grades 3-4) in Patients Treated with ENHERTU in DESTINY-Breast03
Adverse Reactions | ENHERTU 5.4 mg/kg N=257 |  | Ado-trastuzumab emtansine 3.6 mg/kg N=261
Adverse Reactions | All Grades % | Grades 3-4 % | All Grades % | Grades 3-4 %
Gastrointestinal Disorders
Nausea | 76 | 7 | 30 | 0.4
Vomiting | 49 | 1.6 | 10 | 0.8
Constipation | 34 | 0 | 20 | 0
Diarrhea | 29 | 1.2 | 7 | 0.4
Abdominal pain [Including abdominal pain, abdominal discomfort, lower abdominal pain, and upper abdominal pain] | 21 | 0.8 | 8 | 0.4
Stomatitis [Including stomatitis, aphthous ulcer, mouth ulceration, oral mucosa erosion, and oral mucosal eruption] | 20 | 0.8 | 5 | 0
Dyspepsia | 11 | 0 | 6 | 0
General Disorders and Administration Site Conditions
Fatigue [Including fatigue, asthenia, malaise, and lethargy] | 49 | 6 | 35 | 0.8
Skin and Subcutaneous Tissue Disorders
Alopecia [This Grade 3 event was reported by the investigator. Per NCI CTCAE v.5.0, the highest NCI CTCAE grade for alopecia is Grade 2.] | 37 | 0.4 | 3.1 | 0
Musculoskeletal and Connective Tissue Disorders
Musculoskeletal pain [Including back pain, myalgia, pain in extremity, musculoskeletal pain, muscle spasms, bone pain, neck pain, musculoskeletal chest pain, and limb discomfort] | 31 | 1.2 | 25 | 0.4
Metabolism and Nutrition Disorders
Decreased appetite | 29 | 1.6 | 17 | 0.4
Investigations
Decreased weight | 17 | 1.2 | 6 | 0.4
Respiratory, Thoracic, and Mediastinal Disorders
Respiratory infection [Including respiratory tract infection, lower and upper respiratory tract infection, pneumonia, influenza, influenza-like illness, viral upper respiratory infection, bronchitis, and respiratory syncytial virus infection] | 22 | 0.8 | 12 | 1.1
Epistaxis | 11 | 0 | 16 | 0.4
Cough | 11 | 0.4 | 10 | 0
Interstitial lung disease [Interstitial lung disease includes events that were adjudicated as drug-induced ILD for ENHERTU: pneumonitis, interstitial lung disease, organizing pneumonia, pneumonia, and pulmonary mass. For ado-trastuzumab emtansine: pneumonitis, interstitial lung disease, organizing pneumonia, and pulmonary embolism.] | 11 | 0.8 | 1.9 | 0
Nervous System Disorders
Headache [Including headache and migraine] | 22 | 0.4 | 16 | 0
Peripheral neuropathy [Including peripheral neuropathy, peripheral sensory neuropathy, and paresthesia] | 13 | 0.4 | 14 | 0.4
Dizziness | 13 | 0.4 | 8 | 0
Events were graded using NCI CTCAE version 5.0.

Other clinically relevant adverse reactions reported in less than 10% of patients in the ENHERTU-treated group were:

- Respiratory, Thoracic, and Mediastinal Disorders: dyspnea (8%)
- Skin and Subcutaneous Tissue Disorders: pruritus (8%) and skin hyperpigmentation (6%) [including skin hyperpigmentation, skin discoloration, and pigmentation disorder]
- Nervous System Disorders: dysgeusia (6%)
- Metabolism and Nutrition Disorders: dehydration (4.3%)
- Eye Disorders: blurred vision (3.5%)
- Cardiac Disorders: asymptomatic left ventricular ejection fraction decrease (2.7%) [see Warnings and Precautions (5.3)]
- Injury, Poisoning, and Procedural Complications: infusion-related reactions (2.3%) [including hypersensitivity and infusion-related reactions]
- Blood and Lymphatic System Disorders: febrile neutropenia (0.8%)

Table 7: Selected Laboratory Abnormalities in Patients in DESTINY-Breast03
Laboratory Parameter | ENHERTU 5.4 mg/kg N=257 |  | Ado-trastuzumab emtansine 3.6 mg/kg N=261
Laboratory Parameter | All Grades % | Grades 3-4 % | All Grades % | Grades 3-4 %
Hematology
Decreased white blood cell count | 74 | 8 | 24 | 0.8
Decreased neutrophil count | 70 | 18 | 30 | 2.3
Decreased hemoglobin | 64 | 7 | 38 | 6
Decreased lymphocyte count | 55 | 14 | 23 | 3.9
Decreased platelet count | 52 | 7 | 79 | 24
Chemistry
Increased aspartate aminotransferase | 67 | 0.8 | 83 | 5
Increased alanine aminotransferase | 53 | 1.6 | 67 | 6
Increased blood alkaline phosphatase | 49 | 0.8 | 46 | 0.8
Decreased blood potassium | 35 | 4.7 | 39 | 1.5
Increased blood bilirubin | 20 | 0 | 14 | 0
Increased blood creatinine | 16 | 0.8 | 8 | 0.4
Percentages were calculated using patients with worsening laboratory values from baseline and the number of patients with both baseline and post-treatment measurements as the denominator.
Frequencies were based on NCI CTCAE v.5.0 grade-derived laboratory abnormalities.

DESTINY-Breast02

The safety of ENHERTU was evaluated in 404 patients with unresectable or metastatic HER2-positive breast cancer who received at least one dose of ENHERTU 5.4 mg/kg in DESTINY-Breast02 [see Clinical Studies (14.1)]. ENHERTU was administered by intravenous infusion once every three weeks. The median duration of treatment was 11 months (range: 0.7 to 45) for patients who received ENHERTU.

Serious adverse reactions occurred in 26% of patients receiving ENHERTU. Serious adverse reactions in >1% of patients who received ENHERTU were COVID-19, ILD, pneumonia, vomiting, fatigue, and nausea. Fatalities due to adverse reactions occurred in 2.5% of patients including pneumonitis (2 patients), acute myeloid leukemia, brain edema, COVID-19, hemorrhage, hepatitis B, malignant pleural effusion, pneumonia, and vasogenic cerebral edema (one patient each).

ENHERTU was permanently discontinued in 20% of patients, of which ILD accounted for 9%. Dose interruptions due to adverse reactions occurred in 45% of patients treated with ENHERTU. The most frequent adverse reactions (>2%) associated with dose interruption were neutropenia, COVID-19, anemia, fatigue, leukopenia, upper respiratory tract infection, and thrombocytopenia. Dose reductions occurred in 25% of patients treated with ENHERTU. The most frequent adverse reactions (>2%) associated with dose reduction were fatigue, nausea, neutropenia, and vomiting.

The most common (≥20%) adverse reactions, including laboratory abnormalities, were nausea, decreased white blood cell count, decreased hemoglobin, decreased neutrophil count, fatigue, decreased lymphocyte count, decreased platelet count, increased alanine aminotransferase, vomiting, increased aspartate aminotransferase, alopecia, increased blood alkaline phosphatase, constipation, decreased appetite, decreased blood potassium, diarrhea, musculoskeletal pain, increased blood bilirubin, abdominal pain, and headache.

Tables 8 and 9 summarize common adverse reactions and laboratory abnormalities observed in DESTINY-Breast02.

Table 8: Common Adverse Reactions (≥10% All Grades or ≥2% Grades 3-4) in Patients Treated with ENHERTU in DESTINY-Breast02
Adverse Reactions | ENHERTU 5.4 mg/kg N=404 |  | Treatment of Physician's Choice N=195
Adverse Reactions | All Grades % | Grades 3-4 % | All Grades % | Grades 3-4 %
Gastrointestinal Disorders
Nausea | 73 | 7 | 37 | 2.6
Vomiting | 38 | 3.7 | 13 | 1
Constipation | 35 | 0.3 | 11 | 0.5
Diarrhea | 27 | 2.7 | 54 | 7
Abdominal pain [Including abdominal discomfort, abdominal pain, upper abdominal pain, lower abdominal pain, and gastrointestinal pain] | 22 | 1 | 20 | 2.1
Dyspepsia | 12 | 0 | 9 | 0
Stomatitis [Including aphthous ulcer, mouth ulceration, and stomatitis] | 12 | 1 | 21 | 1
General Disorders and Administration Site Conditions
Fatigue [Including asthenia, fatigue, lethargy, and malaise] | 62 | 9 | 37 | 1
Skin and Subcutaneous Tissue Disorders
Alopecia | 37 | 0.3 | 4.1 | 0
Metabolism and Nutrition Disorders
Decreased appetite | 31 | 1.7 | 18 | 0.5
Musculoskeletal and Connective Tissue Disorders
Musculoskeletal pain [Including back pain, bone pain, limb discomfort, musculoskeletal chest pain, musculoskeletal pain, muscle spasms, myalgia, neck pain, and pain in extremity] | 25 | 0.7 | 18 | 0.5
Nervous System Disorders
Headache [Including headache and migraine] | 20 | 0.3 | 6 | 0
Investigations
Decreased weight | 18 | 0.3 | 3.6 | 0
Respiratory, Thoracic, and Mediastinal Disorders
Cough | 13 | 0 | 10 | 0
Interstitial lung disease [Interstitial lung disease includes events that were adjudicated as drug-induced ILD for ENHERTU: pneumonitis, interstitial lung disease, idiopathic interstitial pneumonia, lung disorder, pulmonary toxicity, and pneumonia.] | 10 | 0.7 | 0.5 | 0.5
Events were graded using NCI CTCAE version 5.0.

Other clinically relevant adverse reactions reported in less than 10% of patients in the ENHERTU-treated group were:

- Respiratory, Thoracic, and Mediastinal Disorders: dyspnea (8%) and epistaxis (8%)
- Skin and Subcutaneous Tissue Disorders: rash (8%) [including rash, pustular rash, maculo-papular rash, and pruritic rash], pruritus (5%), skin hyperpigmentation (5%) [including skin hyperpigmentation and pigmentation disorder]
- Nervous System Disorders: dizziness (8%) and dysgeusia (8%)
- Cardiac Disorders: asymptomatic left ventricular ejection fraction decrease (4.2%) [see Warnings and Precautions (5.3)]
- Eye Disorders: dry eye (6%) and blurred vision [including blurred vision and visual impairment] (3%)
- Metabolism and Nutrition Disorders: dehydration (2.7%)
- Injury, Poisoning, and Procedural Complications: infusion-related reactions (1.2%)
- Blood and Lymphatic System Disorders: febrile neutropenia (0.3%)

Table 9: Selected Laboratory Abnormalities in Patients in DESTINY-Breast02
Laboratory Parameter | ENHERTU 5.4 mg/kg N=404 |  | Treatment of Physician's Choice N=195
Laboratory Parameter | All Grades % | Grades 3-4 % | All Grades % | Grades 3-4 %
Hematology
Decreased white blood cell count | 70 | 12 | 42 | 3.2
Decreased hemoglobin | 67 | 9 | 54 | 3.2
Decreased neutrophil count | 64 | 16 | 34 | 4.7
Decreased lymphocyte count | 58 | 17 | 38 | 4.7
Decreased platelet count | 48 | 2.7 | 31 | 1.6
Chemistry
Increased alanine aminotransferase | 43 | 1 | 32 | 1.6
Increased aspartate aminotransferase | 37 | 0.7 | 29 | 2.1
Increased blood alkaline phosphatase | 37 | 0 | 17 | 0
Decreased blood potassium | 30 | 3.7 | 29 | 8
Increased blood bilirubin | 23 | 0.3 | 44 | 2.1
Increased blood creatinine | 7 | 0.3 | 13 | 0
Percentages were calculated using patients with worsening laboratory values from baseline and the number of patients with both baseline and post-treatment measurements as the denominator.
Frequencies were based on NCI CTCAE v.5.0 grade-derived laboratory abnormalities.

DESTINY-Breast01 and Study DS8201-A-J101

The safety of ENHERTU was evaluated in a pooled analysis of 234 patients with unresectable or metastatic HER2-positive breast cancer who received at least one dose of ENHERTU 5.4 mg/kg in DESTINY-Breast01 and Study DS8201-A-J101 (NCT02564900) [see Clinical Studies (14.1)]. ENHERTU was administered by intravenous infusion once every three weeks. The median duration of treatment was 7 months (range: 0.7 to 31).

In the pooled 234 patients, the median age was 56 years (range: 28-96), 74% of patients were <65 years, 99.6% of patients were female, and the majority were White (51%) or Asian (42%). Patients had an Eastern Cooperative Oncology Group (ECOG) performance status of 0 (58%) or 1 (42%) at baseline. Ninety-four percent had visceral disease, 31% had bone metastases, and 13% had brain metastases.

Serious adverse reactions occurred in 20% of patients receiving ENHERTU. Serious adverse reactions in >1% of patients who received ENHERTU were interstitial lung disease, pneumonia, vomiting, nausea, cellulitis, decreased blood potassium, and intestinal obstruction. Fatalities due to adverse reactions occurred in 4.3% of patients including interstitial lung disease (2.6%), and the following events occurred in one patient each (0.4%): acute hepatic failure/acute kidney injury, general physical health deterioration, pneumonia, and hemorrhagic shock.

ENHERTU was permanently discontinued in 9% of patients, of which ILD accounted for 6%.

Dose interruptions due to adverse reactions occurred in 33% of patients treated with ENHERTU. The most frequent adverse reactions (>2%) associated with dose interruption were neutropenia, anemia, thrombocytopenia, leukopenia, upper respiratory tract infection, fatigue, nausea, and ILD.

Dose reductions occurred in 18% of patients treated with ENHERTU. The most frequent adverse reactions (>2%) associated with dose reduction were fatigue, nausea, and neutropenia.

The most common (≥20%) adverse reactions, including laboratory abnormalities, were nausea, decreased white blood cell count, decreased hemoglobin, decreased neutrophil count, fatigue, vomiting, alopecia, increased aspartate aminotransferase, increased alanine aminotransferase, decreased platelet count, constipation, decreased appetite, diarrhea, decreased blood potassium, and cough.

Tables 10 and 11 summarize common adverse reactions and laboratory abnormalities observed in ENHERTU-treated patients in DESTINY-Breast01 and Study DS8201-A-J101.

Table 10: Common Adverse Reactions (≥10% All Grades or ≥2% Grades 3 or 4) in Patients in DESTINY-Breast01 and Study DS8201-A-J101
Adverse Reactions | ENHERTU 5.4 mg/kg N=234
Adverse Reactions | All Grades % | Grades 3 or 4 %
Gastrointestinal Disorders
Nausea | 79 | 7
Vomiting | 47 | 3.8
Constipation | 35 | 0.9
Diarrhea | 29 | 1.7
Abdominal pain [Including abdominal discomfort, gastrointestinal pain, abdominal pain, lower abdominal pain, and upper abdominal pain] | 19 | 1.3
Stomatitis [Including stomatitis, aphthous ulcer, mouth ulceration, oral mucosa erosion, and oral mucosa blistering. One Grade 1 event of aphthous ulcer was not included in the summary of grouped term stomatitis (from DESTINY-Breast01).] | 14 | 0.9
Dyspepsia | 12 | 0
General Disorders and Administration Site Conditions
Fatigue [Including fatigue and asthenia] | 59 | 6
Skin and Subcutaneous Tissue Disorders
Alopecia | 46 | 0.4 [This Grade 3 event was reported by the investigator. Per NCI CTCAE v.4.03, the highest NCI CTCAE grade for alopecia is Grade 2.]
Rash [Including rash, pustular rash, and maculo-papular rash] | 10 | 0
Metabolism and Nutrition Disorders
Decreased appetite | 32 | 1.3
Respiratory, Thoracic, and Mediastinal Disorders
Cough | 20 | 0
Dyspnea | 13 | 1.3
Epistaxis | 13 | 0
Interstitial lung disease [Interstitial lung disease includes events that were adjudicated as drug-induced ILD: pneumonitis, interstitial lung disease, respiratory failure, organizing pneumonia, acute respiratory failure, lung infiltration, lymphangitis, and alveolitis.] | 9 | 2.6 [All events had fatal outcomes (n=6).]
Nervous System Disorders
Headache [Including headache, sinus headache, and migraine] | 19 | 0
Dizziness | 10 | 0
Infections and Infestations
Upper respiratory tract infection [Including influenza, influenza-like illness, and upper respiratory tract infection] | 15 | 0
Eye Disorders
Dry eye | 11 | 0.4 [This Grade 4 event was reported by the investigator. Per NCI CTCAE v.4.03, the highest NCI CTCAE grade for dry eye is Grade 3.]
Events were graded using NCI CTCAE version 4.03.

Other clinically relevant adverse reactions reported in less than 10% of patients were:

- Injury, Poisoning, and Procedural Complications: infusion-related reactions (2.6%)
- Blood and Lymphatic System Disorders: febrile neutropenia (1.7%)

Table 11: Selected Laboratory Abnormalities in Patients with Unresectable or Metastatic HER2-positive Breast Cancer Treated with ENHERTU in DESTINY-Breast01 and Study DS8201-A-J101
Laboratory Parameter | ENHERTU 5.4 mg/kg N=234
Laboratory Parameter | All Grades % | Grades 3 or 4 %
Hematology
Decreased white blood cell count | 70 | 7
Decreased hemoglobin | 70 | 7
Decreased neutrophil count | 62 | 16
Decreased platelet count | 37 | 3.4
Chemistry
Increased aspartate aminotransferase | 41 | 0.9
Increased alanine aminotransferase | 38 | 0.4
Decreased blood potassium | 26 | 3
Percentages were calculated using patients with worsening laboratory values from baseline and the number of patients with both baseline and post-treatment measurements as the denominator.
Frequencies were based on NCI CTCAE v.4.03 grade-derived laboratory abnormalities.

HER2-Low and HER2-Ultralow Metastatic Breast Cancer

DESTINY-Breast06

The safety of ENHERTU was evaluated in 434 patients with unresectable or metastatic HER2-low (IHC 1+ or IHC 2+/ISH-) or HER2-ultralow (IHC 0 with membrane staining) breast cancer who received ENHERTU 5.4 mg/kg in DESTINY-Breast06 [see Clinical Studies (14.2)]. ENHERTU was administered by intravenous infusion once every three weeks. The median duration of treatment was 11 months (range: 0.4 to 39.6) for patients who received ENHERTU.

Serious adverse reactions occurred in 20% of patients receiving ENHERTU. Serious adverse reactions in >1% of patients who received ENHERTU were interstitial lung disease (ILD)/pneumonitis, COVID-19, febrile neutropenia, and hypokalemia. Fatalities due to adverse reactions occurred in 2.8% of patients including ILD (0.7%); sepsis (0.5%); and COVID-19 pneumonia, bacterial meningoencephalitis, neutropenic sepsis, peritonitis, cerebrovascular accident, general physical health deterioration (0.2% each).

ENHERTU was permanently discontinued in 14% of patients. The most frequent adverse reactions (>2%) associated with permanent discontinuation was ILD/pneumonitis.

Dose interruptions due to adverse reactions occurred in 48% of patients treated with ENHERTU. The most frequent adverse reactions (>2%) associated with dose interruption were COVID-19, decreased neutrophil count, anemia, pyrexia, pneumonia, decreased white blood cell count, and ILD.

Dose reductions occurred in 25% of patients treated with ENHERTU. The most frequent adverse reactions (>2%) associated with dose reduction were nausea, fatigue, decreased platelet count, and decreased neutrophil count.

The most common (≥20%) adverse reactions, including laboratory abnormalities, were decreased white blood cell count, decreased neutrophil count, nausea, decreased hemoglobin, decreased lymphocyte count, fatigue, decreased platelet count, alopecia, increased alanine aminotransferase, increased blood alkaline phosphatase, increased aspartate aminotransferase, decreased blood potassium, diarrhea, vomiting, constipation, decreased appetite, COVID-19, and musculoskeletal pain.

Tables 12 and 13 summarize common adverse reactions and laboratory abnormalities observed in DESTINY-Breast06.

Table 12: Common Adverse Reactions (≥10% All Grades or ≥2% Grades 3 or 4) in Patients Treated with ENHERTU in DESTINY-Breast06
Adverse Reactions | ENHERTU 5.4 mg/kg |  | Chemotherapy
Adverse Reactions | N=434 |  | N=417
Adverse Reactions | All Grades % | Grades 3 or 4 % | All Grades % | Grades 3 or 4 %
Gastrointestinal Disorders
Nausea | 70 | 2.1 | 30 | 0.5
Diarrhea | 34 | 2.3 | 27 | 2.6
Vomiting | 34 | 1.4 | 12 | 0.2
Constipation | 32 | 0.7 | 15 | 0.5
Abdominal pain [Including abdominal discomfort, abdominal pain, lower abdominal pain, upper abdominal pain, and gastrointestinal pain] | 20 | 0.5 | 14 | 0.2
Stomatitis [Including stomatitis, aphthous ulcer, mouth ulceration, oral mucosa erosion, oral mucosal blistering, and oral mucosal eruption] | 15 | 0 | 11 | 0.5
Dyspepsia | 12 | 0 | 4.8 | 0
General Disorders and Administration Site Conditions
Fatigue [Including fatigue, asthenia, malaise, and lethargy] | 53 | 4.4 | 40 | 2.4
Pyrexia | 12 | 0.2 | 7 | 0
Skin and Subcutaneous Tissue Disorders
Alopecia | 48 | 0 | 21 | 0.5
Rash [Including dermatitis, dermatitis allergic, dermatitis contact, eczema, palmar-plantar erythrodysesthesia syndrome, rash, rash erythematous, rash macular, rash maculo-papular, rash papular, rash pruritic, rash pustular] | 12 | 0.2 | 43 | 8
Metabolism and Nutrition Disorders
Decreased appetite | 26 | 1.4 | 12 | 0.5
Infections and Infestations
COVID-19 [Including COVID-19, COVID-19 pneumonia] | 26 | 0.9 | 13 | 1
Upper respiratory tract infection [Including influenza, influenza-like illness, upper respiratory tract infection, nasopharyngitis, pharyngitis, sinusitis, rhinitis, laryngitis] | 19 | 0 | 9 | 0
Musculoskeletal and Connective Tissue Disorders
Musculoskeletal pain [Including back pain, myalgia, pain in extremity, musculoskeletal pain, muscle spasms, bone pain, neck pain, musculoskeletal chest pain, and limb discomfort] | 24 | 0.5 | 23 | 1.9
Nervous System Disorders
Headache [Including migraine, headache, and sinus headache] | 18 | 0.5 | 10 | 0
Dysgeusia | 12 | 0.2 | 6 | 0
Respiratory, Thoracic, and Mediastinal Disorders
Cough | 16 | 0 | 9 | 0
Interstitial lung disease [Including bronchiectasis, interstitial lung disease, lower respiratory tract infection, pneumonia, pneumonia bacterial, pneumonitis, and pulmonary toxicity] | 11 | 0.7 | 0.2 | 0
Epistaxis | 10 | 0 | 3.6 | 0.2
Events were graded using NCI CTCAE version 5.0.

Other clinically relevant adverse reactions reported in less than 10% of patients in the ENHERTU-treated group were:

- Nervous System Disorders: dizziness (9%)
- Investigations: decreased weight (7%)
- Eye Disorders: dry eye (7%), and blurred vision (5%)
- Respiratory, Thoracic, and Mediastinal Disorders: dyspnea (6%)
- Gastrointestinal Disorders: abdominal distension (4.8%), flatulence (2.3%), and gastritis (0.7%)
- Skin and Subcutaneous Tissue Disorders: pruritus (3.9%), and skin hyperpigmentation (0.9%)
- Metabolism and Nutrition Disorders: dehydration (1.6%)
- Blood and lymphatic system disorders: febrile neutropenia (1.2%)
- Injury, Poisoning, and Procedural Complications: infusion related reaction (1.2%)

Table 13: Selected Laboratory Abnormalities in Patients in DESTINY-Breast06
Laboratory Parameter | ENHERTU 5.4 mg/kg |  | Chemotherapy
Laboratory Parameter | N=434 |  | N=417
Laboratory Parameter | All Grades % | Grades 3 or 4 % | All Grades % | Grades 3 or 4 %
Hematology
Decreased white blood cell count | 86 | 13 | 71 | 11
Decreased neutrophil count | 75 | 27 | 53 | 20
Decreased hemoglobin | 69 | 9 | 58 | 5
Decreased lymphocyte count | 66 | 19 | 46 | 8
Decreased platelet count | 48 | 6 | 25 | 1
Chemistry
Increased alanine aminotransferase | 44 | 3.2 | 30 | 0.7
Increased blood alkaline phosphatase | 43 | 0.2 | 22 | 0.2
Increased aspartate aminotransferase | 41 | 2.6 | 27 | 1.2
Decreased blood potassium | 35 | 8 | 15 | 2.9
Increased blood bilirubin | 16 | 1.9 | 23 | 1.5
Increased blood creatinine | 10 | 1.9 | 8 | 1
Percentages were calculated using patients with worsening laboratory values from baseline and the number of patients with both baseline and post-treatment measurements as the denominator.
Frequencies were based on NCI CTCAE v.5.0 grade-derived laboratory abnormalities.

DESTINY-Breast04

The safety of ENHERTU was evaluated in 371 patients with unresectable or metastatic HER2-low (IHC 1+ or IHC 2+/ISH-) breast cancer who received ENHERTU 5.4 mg/kg in DESTINY-Breast04 [see Clinical Studies (14.2)]. ENHERTU was administered by intravenous infusion once every three weeks. The median duration of treatment was 8 months (range: 0.2 to 33) for patients who received ENHERTU.

Serious adverse reactions occurred in 28% of patients receiving ENHERTU. Serious adverse reactions in >1% of patients who received ENHERTU were ILD/pneumonitis, pneumonia, dyspnea, musculoskeletal pain, sepsis, anemia, febrile neutropenia, hypercalcemia, nausea, pyrexia, and vomiting. Fatalities due to adverse reactions occurred in 4.0% of patients including ILD/pneumonitis (3 patients); sepsis (2 patients); and ischemic colitis, disseminated intravascular coagulation, dyspnea, febrile neutropenia, general physical health deterioration, pleural effusion, and respiratory failure (1 patient each).

ENHERTU was permanently discontinued in 16% of patients, of which ILD/pneumonitis accounted for 8%. Dose interruptions due to adverse reactions occurred in 39% of patients treated with ENHERTU. The most frequent adverse reactions (>2%) associated with dose interruption were neutropenia, fatigue, anemia, leukopenia, COVID-19, ILD/pneumonitis, increased transaminases, and hyperbilirubinemia. Dose reductions occurred in 23% of patients treated with ENHERTU. The most frequent adverse reactions (>2%) associated with dose reduction were fatigue, nausea, thrombocytopenia, and neutropenia.

The most common (≥20%) adverse reactions, including laboratory abnormalities, were nausea, decreased white blood cell count, decreased hemoglobin, decreased neutrophil count, decreased lymphocyte count, fatigue, decreased platelet count, alopecia, vomiting, increased aspartate aminotransferase, increased alanine aminotransferase, constipation, increased blood alkaline phosphatase, decreased appetite, musculoskeletal pain, diarrhea, and decreased blood potassium.

Tables 14 and 15 summarize common adverse reactions and laboratory abnormalities observed in DESTINY-Breast04.

Table 14: Common Adverse Reactions (≥10% All Grades or ≥2% Grades 3 or 4) in Patients Treated with ENHERTU in DESTINY-Breast04
Adverse Reactions | ENHERTU 5.4 mg/kg |  | Chemotherapy
Adverse Reactions | N=371 |  | N=172
Adverse Reactions | All Grades % | Grades 3 or 4 % | All Grades % | Grades 3 or 4 %
Gastrointestinal Disorders
Nausea | 76 | 4.6 | 30 | 0
Vomiting | 40 | 1.6 | 13 | 0
Constipation | 34 | 0.8 | 22 | 0
Diarrhea | 27 | 1.3 | 22 | 1.7
Abdominal pain [Including abdominal pain, abdominal discomfort, lower abdominal pain, and upper abdominal pain] | 18 | 0.5 | 13 | 0
Stomatitis [Including stomatitis, aphthous ulcer, mouth ulceration, and pharyngeal inflammation] | 13 | 0.3 | 12 | 0.6
General Disorders and Administration Site Conditions
Fatigue [Including fatigue, asthenia, and malaise] | 54 | 9 | 48 | 4.7
Pyrexia | 12 | 0.3 | 13 | 0
Skin and Subcutaneous Tissue Disorders
Alopecia | 40 | 0 | 33 | 0
Rash [Including rash, pustular rash, pruritic rash, maculo-papular rash, palmar-plantar erythrodysesthesia syndrome, papular rash, macular rash, eczema, erythema multiforme, dermatitis, urticarial dermatitis, drug eruption, and dermatitis bullous] | 13 | 0 | 23 | 4.7
Metabolism and Nutrition Disorders
Decreased appetite | 32 | 2.4 | 19 | 1.2
Musculoskeletal and Connective Tissue Disorders
Musculoskeletal pain [Including back pain, myalgia, pain in extremity, musculoskeletal pain, bone pain, musculoskeletal chest pain, arthralgia, noncardiac chest pain, musculoskeletal stiffness, arthritis, spinal pain, and neck pain] | 32 | 1.3 | 31 | 0.6
Investigations
Decreased weight | 16 | 0.3 | 8 | 0
Vascular Disorders
Hemorrhage [Including esophageal varices, hemorrhage, hemorrhoidal hemorrhage, epistaxis, hematuria, conjunctival hemorrhage, vaginal hemorrhage, gingival bleeding, genital hemorrhage, eye hemorrhage, hemoptysis, hemorrhagic cystitis, pharyngeal hemorrhage, rectal hemorrhage, upper gastrointestinal hemorrhage, and esophageal hemorrhage] | 16 | 0 | 3.5 | 0
Nervous System Disorders
Headache [Including headache and migraine] | 15 | 0.3 | 6 | 0
Peripheral neuropathy [Including peripheral neuropathy, peripheral sensory neuropathy, peripheral motor neuropathy, polyneuropathy, paresthesia, hypoesthesia, dysesthesia, and neuralgia] | 13 | 0 | 29 | 5
Dizziness [Including dizziness, postural dizziness, and vertigo] | 11 | 0.5 | 6 | 0
Infections and Infestations
Upper respiratory tract infection [Including upper respiratory tract infection, influenza, influenza-like illness, nasopharyngitis, pharyngitis, sinusitis, and rhinitis] | 14 | 0.3 | 5 | 0
Respiratory, Thoracic and Mediastinal Disorders
Interstitial lung disease [Interstitial lung disease includes events that were adjudicated as drug-induced ILD for ENHERTU: interstitial lung disease, pneumonitis, organizing pneumonia, pneumonia, and radiation pneumonitis.] | 12 | 1.3 | 0.6 | 0
Dyspnea | 10 | 1.3 | 9 | 1.2
Events were graded using NCI CTCAE version 5.0.

Other clinically relevant adverse reactions reported in less than 10% of patients treated with ENHERTU:

- Nervous System Disorders: dysgeusia (10%)
- Respiratory, Thoracic and Mediastinal Disorders: cough (10%)
- Gastrointestinal Disorders: abdominal distension (5%), gastritis (2.7%), flatulence (2.4%)
- Eye Disorders: blurred vision (4.9%) [including blurred vision and visual impairment]
- Skin and Subcutaneous Tissue Disorders: pruritus (3.2%) and skin hyperpigmentation (2.7%) [including skin hyperpigmentation, skin discoloration, and pigmentation disorder]
- Metabolism and Nutrition Disorders: dehydration (1.9%)
- Blood and Lymphatic System Disorders: febrile neutropenia (1.1%)
- Injury, Poisoning, and Procedural Complications: infusion-related reactions (0.5%) [including injection-site reaction and chills]

Table 15: Selected Laboratory Abnormalities in Patients in DESTINY-Breast04
Laboratory Parameter | ENHERTU 5.4 mg/kg |  | Chemotherapy
Laboratory Parameter | N=371 |  | N=172
Laboratory Parameter | All Grades % | Grades 3 or 4 % | All Grades % | Grades 3 or 4 %
Hematology
Decreased white blood cell count | 70 | 9 | 78 | 25
Decreased hemoglobin | 64 | 8 | 53 | 6
Decreased neutrophil count | 64 | 14 | 73 | 38
Decreased lymphocyte count | 55 | 18 | 40 | 11
Decreased platelet count | 44 | 6 | 21 | 0.6
Chemistry
Increased aspartate aminotransferase | 38 | 2.2 | 38 | 4.1
Increased alanine aminotransferase | 36 | 0.8 | 38 | 4.1
Increased blood alkaline phosphatase | 34 | 0.3 | 24 | 0
Decreased blood potassium | 25 | 3.3 | 17 | 1.2
Increased blood bilirubin | 16 | 2.7 | 15 | 0.6
Increased blood creatinine | 15 | 1.1 | 9 | 0.6
Percentages were calculated using patients with worsening laboratory values from baseline and the number of patients with both baseline and post-treatment measurements as the denominator.
Frequencies were based on NCI CTCAE v.5.0 grade-derived laboratory abnormalities.

HER2-Mutant Unresectable or Metastatic NSCLC

DESTINY-Lung02 evaluated two dose levels (5.4 mg/kg [n=101] and 6.4 mg/kg [n=50]); however, only the results for the recommended dose of 5.4 mg/kg intravenously every 3 weeks are described below due to increased toxicity observed with the higher dose in patients with NSCLC, including ILD/pneumonitis.

The safety of ENHERTU was evaluated in 101 patients in DESTINY-Lung02 [see Clinical Studies (14.3)]. Patients received ENHERTU 5.4 mg/kg intravenously once every three weeks until disease progression or unacceptable toxicity. Nineteen percent of patients were exposed for greater than 6 months. The median age was 59 years (range 30 to 83); 64% were female; 23% were White, 64% were Asian, and 14% were other races.

Serious adverse reactions occurred in 30% of patients receiving ENHERTU. Serious adverse reactions in >1% of patients who received ENHERTU were ILD/pneumonitis, thrombocytopenia, dyspnea, nausea, pleural effusion, and increased troponin I. Fatality occurred in 1 patient with suspected ILD/pneumonitis (1%).

ENHERTU was permanently discontinued due to an adverse reaction in 8% of patients. Adverse reactions which resulted in permanent discontinuation of ENHERTU were ILD/pneumonitis, diarrhea, decreased blood potassium, hypomagnesemia, myocarditis, and vomiting.

Dose interruptions of ENHERTU due to adverse reactions occurred in 23% of patients. Adverse reactions which required dose interruption (>2%) included neutropenia and ILD/pneumonitis.

Dose reductions due to an adverse reaction occurred in 11% of patients.

The most common (≥20%) adverse reactions, including laboratory abnormalities, were nausea, decreased white blood cell count, decreased hemoglobin, decreased neutrophil count, decreased lymphocyte count, decreased platelet count, decreased albumin, increased aspartate aminotransferase, increased alanine aminotransferase, fatigue, constipation, decreased appetite, vomiting, increased alkaline phosphatase, and alopecia.

Tables 16 and 17 summarize common adverse reactions and laboratory abnormalities observed in DESTINY-Lung02.

Table 16: Common Adverse Reactions (≥10% All Grades or ≥2% Grades 3 or 4) in Patients with Unresectable or Metastatic HER2-Mutant NSCLC in DESTINY-Lung02
Adverse Reactions | ENHERTU 5.4 mg/kg N=101
Adverse Reactions | All Grades % | Grades 3 or 4 %
Gastrointestinal Disorders
Nausea | 61 | 3
Constipation | 31 | 1
Vomiting [Including vomiting and retching] | 26 | 2
Diarrhea | 19 | 1
Stomatitis [Including mucosal inflammation and stomatitis] | 12 | 0
General Disorders and Administration Site Conditions
Fatigue [Including asthenia, fatigue, and malaise] | 32 | 4
Metabolism and Nutrition Disorders
Decreased appetite | 30 | 1
Skin and Subcutaneous Tissue Disorders
Alopecia | 21 | 0
Musculoskeletal and Connective Tissue Disorders
Musculoskeletal pain [Including back pain, musculoskeletal stiffness, musculoskeletal chest pain, arthralgia, musculoskeletal pain, myalgia, and pain in extremity] | 15 | 1
Events were graded using NCI CTCAE version 5.0.

Other clinically relevant adverse reactions reported in less than 10% of patients were:

- Respiratory, Thoracic and Mediastinal Disorders: interstitial lung disease (6%) [including interstitial lung disease that was adjudicated as drug-induced ILD including pneumonitis, interstitial lung disease, pulmonary toxicity, and respiratory failure], dyspnea (5%), and epistaxis (3%)
- Gastrointestinal Disorders: abdominal pain (9%) [including abdominal discomfort, abdominal pain, and upper abdominal pain]
- Skin and Subcutaneous Disorders: rash (3%) [including rash and maculo-papular rash]
- Infections and Infestations: upper respiratory tract infection (4%) [including upper respiratory tract infection, pharyngitis, and laryngitis]
- Nervous System Disorders: headache (4%) [including headache and migraine]

Table 17: Select Laboratory Abnormalities in Patients with Unresectable or Metastatic HER2-Mutant NSCLC in DESTINY-Lung02
Laboratory Parameter | ENHERTU 5.4 mg/kg N=101 [Percentages were calculated using patients with worsening laboratory values from baseline and the number of patients with both baseline and post-treatment measurements as the denominator.]
Laboratory Parameter | All Grades [Frequencies were based on NCI CTCAE v.5.0 grade-derived laboratory abnormalities.] % | Grades 3 or 4 %
Hematology [The denominator used to calculate the rate varied from 98 to 99 based on the number of patients with a baseline value and at least one post-treatment value.]
Decreased white blood cell count | 60 | 4
Decreased hemoglobin | 58 | 10
Decreased neutrophil count | 52 | 12
Decreased lymphocyte count | 43 | 16
Decreased platelet count | 40 | 4
Chemistry
Decreased albumin | 39 | 0
Increased aspartate aminotransferase | 35 | 1
Increased alanine aminotransferase | 34 | 2
Increased alkaline phosphatase | 22 | 0
Decreased blood potassium | 17 | 2

HER2-Positive Locally Advanced or Metastatic Gastric Cancer

The safety of ENHERTU was evaluated in 187 patients with locally advanced or metastatic HER2-positive gastric or GEJ adenocarcinoma in DESTINY-Gastric01 [see Clinical Studies (14.4)]. Patients intravenously received at least one dose of either ENHERTU (N=125) 6.4 mg/kg once every three weeks or either irinotecan (N=55) 150 mg/m^2 biweekly or paclitaxel (N=7) 80 mg/m^2 weekly for 3 weeks. The median duration of treatment was 4.6 months (range: 0.7 to 22.3) in the ENHERTU group and 2.8 months (range: 0.5 to 13.1) in the irinotecan/paclitaxel group.

Serious adverse reactions occurred in 44% of patients receiving ENHERTU 6.4 mg/kg. Serious adverse reactions in >2% of patients who received ENHERTU were decreased appetite, ILD, anemia, dehydration, pneumonia, cholestatic jaundice, pyrexia, and tumor hemorrhage. Fatalities due to adverse reactions occurred in 2.4% of patients: disseminated intravascular coagulation, large intestine perforation, and pneumonia occurred in one patient each (0.8%).

ENHERTU was permanently discontinued in 15% of patients, of which ILD accounted for 6%.

Dose interruptions due to adverse reactions occurred in 62% of patients treated with ENHERTU. The most frequent adverse reactions (>2%) associated with dose interruption were neutropenia, anemia, decreased appetite, leukopenia, fatigue, thrombocytopenia, ILD, pneumonia, lymphopenia, upper respiratory tract infection, diarrhea, and decreased blood potassium.

Dose reductions occurred in 32% of patients treated with ENHERTU. The most frequent adverse reactions (>2%) associated with dose reduction were neutropenia, decreased appetite, fatigue, nausea, and febrile neutropenia.

The most common (≥20%) adverse reactions, including laboratory abnormalities, were decreased hemoglobin, decreased white blood cell count, decreased neutrophil count, decreased lymphocyte count, decreased platelet count, nausea, decreased appetite, increased aspartate aminotransferase, fatigue, increased blood alkaline phosphatase, increased alanine aminotransferase, diarrhea, decreased blood potassium, vomiting, constipation, increased blood bilirubin, pyrexia, and alopecia.

Tables 18 and 19 summarize adverse reactions and laboratory abnormalities observed in patients receiving ENHERTU 6.4 mg/kg in DESTINY-Gastric01.

Table 18: Adverse Reactions in ≥10% All Grades or ≥2% Grades 3 or 4 of Patients Receiving ENHERTU in DESTINY-Gastric01
 | ENHERTU 6.4 mg/kg N=125 |  | Irinotecan or Paclitaxel N=62
Adverse Reactions | All Grades % | Grades 3 or 4 % | All Grades % | Grades 3 or 4 %
Adverse Reactions | Gastrointestinal Disorders
Adverse Reactions | Nausea | 63 | 4.8 | 47 | 1.6
Diarrhea | 32 | 2.4 | 32 | 1.6
Vomiting | 26 | 0 | 8 | 0
Constipation | 24 | 0 | 23 | 0
Abdominal pain [Including abdominal discomfort, gastrointestinal pain, abdominal pain, lower abdominal pain, and upper abdominal pain] | 14 | 0.8 | 15 | 3.2
Stomatitis [Including stomatitis, aphthous ulcer, mouth ulceration, oral mucosa erosion, and oral mucosal blistering] | 11 | 1.6 | 4.8 | 0
Metabolism and Nutrition Disorders
Decreased appetite | 60 | 17 | 45 | 13
Dehydration | 6 | 2.4 | 3.2 | 1.6
Blood and Lymphatic System Disorders
Febrile neutropenia | 4.8 | 4.8 | 3.2 | 3.2
General Disorders and Administration Site Conditions
Fatigue [Including fatigue, asthenia, and malaise] | 55 | 9 | 44 | 4.8
Pyrexia | 24 | 0 | 16 | 0
Peripheral edema | 10 | 0 | 0 | 0
Skin and Subcutaneous Tissue Disorders
Alopecia | 22 | 0 | 15 | 0
Respiratory, Thoracic and Mediastinal Disorders
Interstitial lung disease [Interstitial lung disease includes events that were adjudicated as drug-induced ILD: pneumonitis, interstitial lung disease, respiratory failure, organizing pneumonia, acute respiratory failure, lung infiltration, lymphangitis, and alveolitis.] | 10 | 2.4 | 0 | 0
Hepatobiliary Disorders
Abnormal hepatic function | 8 | 3.2 | 1.6 | 1.6
Events were graded using NCI CTCAE version 4.03.

Other clinically relevant adverse reactions reported in less than 10% of patients were:

- Cardiac Disorders: asymptomatic left ventricular ejection fraction decrease (8%) [see Warnings and Precautions (5.3)]
- Infections and Infestations: pneumonia (6%)
- Injury, Poisoning, and Procedural Complications: infusion-related reactions (1.6%)

Table 19: Selected Laboratory Abnormalities Occurring in Patients Receiving ENHERTU in DESTINY-Gastric01
Laboratory Parameter | ENHERTU 6.4 mg/kg N=125 |  | Irinotecan or Paclitaxel N=62
Laboratory Parameter | All Grades % | Grades 3 or 4 % | All Grades % | Grades 3 or 4 %
Hematology
Decreased hemoglobin | 75 | 38 | 55 | 23
Decreased white blood cell count | 74 | 29 | 53 | 13
Decreased neutrophil count | 72 | 51 | 45 | 23
Decreased lymphocyte count | 70 | 28 | 53 | 12
Decreased platelet count | 68 | 12 | 12 | 5
Chemistry
Increased aspartate aminotransferase | 58 | 9 | 32 | 8
Increased blood alkaline phosphatase | 54 | 8 | 34 | 10
Increased alanine aminotransferase | 47 | 9 | 17 | 1.7
Decreased blood potassium | 30 | 4.8 | 18 | 8
Increased blood bilirubin | 24 | 7 | 5 | 3.4
Percentages were calculated using patients with worsening laboratory values from baseline and the number of patients with both baseline and post-treatment measurements as the denominator.
Frequencies were based on NCI CTCAE v.4.03 grade-derived laboratory abnormalities.

HER2-Positive (IHC 3+) Unresectable or Metastatic Solid Tumors

The safety of ENHERTU was evaluated in 347 adult patients with unresectable or metastatic HER2-positive (IHC 3+) solid tumors who received ENHERTU 5.4 mg/kg in DESTINY-Breast01, DESTINY-PanTumor02, DESTINY-Lung01, and DESTINY-CRC02 [see Clinical Studies (14.1 and 14.5)]. ENHERTU was administered by intravenous infusion once every three weeks. The median duration of treatment was 8.3 months (range 0.7 to 30.2).

The median age was 60 years (range 23 to 96); 74% were female; 51% were White, 42% were Asian, 2.9% were Black or African American, 3.5% were of Hispanic or Latino ethnicity; and 40% had an ECOG performance status 0 and 41% had an ECOG performance status of 1.

Serious adverse reactions occurred in 34% of patients receiving ENHERTU. Serious adverse reactions in >1% of patients who received ENHERTU were sepsis, pneumonia, vomiting, urinary tract infection, abdominal pain, nausea, pneumonitis, pleural effusion, hemorrhage, COVID-19, fatigue, acute kidney injury, anemia, cellulitis, and dyspnea. Fatalities due to adverse reactions occurred in 6.3% of patients including ILD/pneumonitis (2.3%), cardiac arrest (0.6%), COVID-19 (0.6%), and sepsis (0.6%). The following events occurred in one patient each (0.3%): acute kidney injury, cerebrovascular accident, general physical health deterioration, pneumonia, and hemorrhagic shock.

ENHERTU was permanently discontinued in 15% of patients, of which ILD/pneumonitis accounted for 10%.

Dose interruptions due to adverse reactions occurred in 48% of patients. The most frequent adverse reactions (>2%) associated with dose interruption were decreased neutrophil count, anemia, COVID-19, fatigue, decreased white blood cell count, and ILD/pneumonitis.

Dose reductions occurred in 27% of patients treated with ENHERTU. The most frequent adverse reactions (>2%) associated with dose reduction were fatigue, nausea, decreased neutrophil count, ILD/pneumonitis, and diarrhea.

The most common (≥20%) adverse reactions, including laboratory abnormalities, were decreased white blood cell count, nausea, decreased hemoglobin, decreased neutrophil count, fatigue, decreased lymphocyte count, decreased platelet count, increased aspartate aminotransferase, increased alanine aminotransferase, increased blood alkaline phosphatase, vomiting, decreased appetite, alopecia, diarrhea, decreased blood potassium, constipation, decreased sodium, stomatitis, and upper respiratory tract infection.

Tables 20 and 21 summarize the common adverse reactions and laboratory abnormalities in DESTINY-PanTumor02, DESTINY-Lung01, DESTINY-Breast01, and DESTINY-CRC02.

Table 20: Common Adverse Reactions (≥10% All Grades or ≥2% Grades 3 or 4) in HER2-positive (IHC 3+) Patients Treated with ENHERTU in DESTINY-Breast01, DESTINY-PanTumor02, DESTINY-Lung01, and DESTINY-CRC02
Adverse Reactions | ENHERTU 5.4 mg/kg N= 347
Adverse Reactions | All Grades % | Grade 3 or 4 %
Gastrointestinal Disorders
Nausea | 69 | 7
Vomiting | 35 | 3.5
Diarrhea | 31 | 4.3
Constipation | 28 | 0.6
Stomatitis [Including stomatitis, mucosal inflammation, aphthous ulcer, mouth ulceration, oral mucosa erosion, oral mucosal blistering, oral mucosal eruption, tongue ulceration, cheilitis.] | 20 | 0.9
Abdominal pain [Including abdominal discomfort, abdominal pain, lower abdominal pain, upper abdominal pain, gastrointestinal pain.] | 18 | 2
Dyspepsia | 12 | 0.3
General Disorders and Administration Site Conditions
Fatigue [Including fatigue, asthenia, malaise, lethargy.] | 59 | 10
Pyrexia | 11 | 0
Edema [Including peripheral edema, edema, localized edema, face edema, skin edema, periorbital edema, eyelid edema] | 11 | 0.6
Metabolism and Nutrition Disorders
Decreased appetite | 34 | 2.6
Skin and Subcutaneous Tissue Disorders
Alopecia | 34 | 0.3
Rash [Including rash, pustular rash, maculo-papular rash, papular rash, macular rash, pruritic rash dermatitis acneiform, dermatitis, eczema, palmar-plantar erythrodysesthesia syndrome.] | 13 | 0.6
Infections and Infestations
Upper respiratory tract infection [Including influenza, influenza-like illness, upper respiratory tract infection, nasopharyngitis, pharyngitis, sinusitis, rhinitis, laryngitis.] | 20 | 0
Pneumonia | 6 | 2.3
Musculoskeletal and Connective Tissue Disorders
Musculoskeletal pain [Including back pain, myalgia, pain in extremity, musculoskeletal pain, muscle spasms, bone pain, neck pain, musculoskeletal chest pain, limb discomfort.] | 19 | 0.3
Respiratory, Thoracic and Mediastinal Disorders
Cough [Including cough, productive cough, upper-airway cough syndrome] | 18 | 0
Interstitial lung disease [Interstitial lung disease includes events that were adjudicated as drug-induced ILD: pneumonitis, ILD, organizing pneumonia, respiratory failure, acute respiratory failure, alveolitis, lung opacity, lymphangitis, pneumonia, bacterial pneumonia, pulmonary fibrosis, and radiation pneumonitis. Grade 5 adjudicated drug-induced ILD events were pneumonitis, respiratory failure, acute respiratory failure, lymphangitis, pulmonary fibrosis.] | 16 | 0.6
Dyspnea [Including dyspnea, exertional dyspnea] | 12 | 1.7
Nervous System Disorders
Headache [Including migraine, headache, sinus headache.] | 15 | 0
Investigations
Decreased weight | 10 | 0.3

Other clinically relevant adverse reactions reported in less than 10% of patients were:

- Respiratory, Thoracic, and Mediastinal Disorders: epistaxis (9%)
- Nervous System Disorders: dizziness (9%) [including dizziness, postural dizziness, and vertigo] and dysgeusia (6%)
- Skin and Subcutaneous Disorders: pruritus (5%) and skin hyperpigmentation (4.3%) [including skin hyperpigmentation, skin discoloration, pigmentation disorder]
- Eye Disorders: blurred vision (4%) [including blurred vision, visual impairment]
- Metabolism and Nutrition Disorders: dehydration (3.2%)
- Gastrointestinal Disorders: abdominal distension (2.6%), flatulence (1.7%) and gastritis (0.9%)
- Blood and Lymphatic System Disorders: febrile neutropenia (1.7%)
- Injury, Poisoning, and Procedural Complications: infusion-related reactions (1.4%) [including administration related reaction, anaphylactic reaction, hypersensitivity, infusion-related reaction and infusion-related hypersensitivity reaction]

Table 21: Selected Laboratory Abnormalities in HER2-positive (IHC 3+) Patients Treated with ENHERTU in DESTINY-Breast01, DESTINY-PanTumor02, DESTINY-Lung01, and DESTINY-CRC02
Laboratory Parameter | ENHERTU 5.4 mg/kg N= 347 [Percentages were calculated using the number of patients with worsening laboratory values from baseline and the number of patients with both baseline and post-treatment measurements as the denominator.]
 | All Grades % | Grades 3 or 4 %
Hematology
Decreased white blood cell count | 75 | 11
Decreased hemoglobin | 67 | 10
Decreased neutrophil count | 66 | 21
Decreased lymphocyte count | 58 | 21
Decreased platelet count | 51 | 7
Chemistry
Increased aspartate aminotransferase | 45 | 1.5
Increased alanine aminotransferase | 44 | 1.5
Increased blood alkaline phosphatase | 36 | 1.2
Decreased blood potassium | 29 | 6
Decreased sodium | 22 | 2.9
Increased blood bilirubin | 15 | 0.6
Increased blood creatinine | 14 | 0.6

8 USE IN SPECIFIC POPULATIONS

8.1 Pregnancy

Risk Summary

Based on its mechanism of action, ENHERTU can cause fetal harm when administered to a pregnant woman. There are no available data on the use of ENHERTU in pregnant women. In postmarketing reports, use of a HER2-directed antibody during pregnancy resulted in cases of oligohydramnios manifesting as fatal pulmonary hypoplasia, skeletal abnormalities, and neonatal death (see Data). Based on its mechanism of action, the topoisomerase inhibitor component of ENHERTU, DXd, can also cause embryo-fetal harm when administered to a pregnant woman because it is genotoxic and targets actively dividing cells [see Clinical Pharmacology (12.1), Nonclinical Toxicology (13.1)]. Advise patients of the potential risks to a fetus.

There are clinical considerations if ENHERTU is used in pregnant women, or if a patient becomes pregnant within 7 months after the last dose of ENHERTU (see Clinical Considerations).

The estimated background risk of major birth defects and miscarriage for the indicated population is unknown. All pregnancies have a background risk of birth defect, loss, or other adverse outcomes. In the U.S. general population, the estimated background risk of major birth defects and miscarriage in clinically recognized pregnancies is 2 to 4% and 15 to 20%, respectively.

Clinical Considerations

Fetal/Neonatal Adverse Reactions

Monitor women who received ENHERTU during pregnancy or within 7 months prior to conception for oligohydramnios. If oligohydramnios occurs, perform fetal testing that is appropriate for gestational age and consistent with community standards of care.

Data

Human Data

There are no available data on the use of ENHERTU in pregnant women. In postmarketing reports in pregnant women receiving a HER2-directed antibody, cases of oligohydramnios manifesting as fatal pulmonary hypoplasia, skeletal abnormalities, and neonatal death have been reported. These case reports described oligohydramnios in pregnant women who received a HER2-directed antibody either alone or in combination with chemotherapy. In some case reports, amniotic fluid index increased after use of a HER2-directed antibody was stopped.

Animal Data

There were no animal reproductive or developmental toxicity studies conducted with fam-trastuzumab deruxtecan-nxki.

8.2 Lactation

Risk Summary

There is no data regarding the presence of fam-trastuzumab deruxtecan-nxki in human milk, the effects on the breastfed child, or the effects on milk production. Because of the potential for serious adverse reactions in a breastfed child, advise women not to breastfeed during treatment with ENHERTU and for 7 months after the last dose.

8.3 Females and Males of Reproductive Potential

Pregnancy Testing

Verify pregnancy status of females of reproductive potential prior to initiation of ENHERTU.

Contraception

Females

ENHERTU can cause fetal harm when administered to a pregnant woman [see Use in Specific Populations (8.1)]. Advise females of reproductive potential to use effective contraception during treatment with ENHERTU and for 7 months after the last dose.

Males

Because of the potential for genotoxicity, advise male patients with female partners of reproductive potential to use effective contraception during treatment with ENHERTU and for 4 months after the last dose [see Nonclinical Toxicology (13.1)].

Infertility

Based on findings in animal toxicity studies, ENHERTU may impair male reproductive function and fertility [see Nonclinical Toxicology (13.1)].

8.4 Pediatric Use

Safety and effectiveness of ENHERTU have not been established in pediatric patients.

Animal Data

Juvenile animal studies have not been conducted with fam-trastuzumab deruxtecan-nxki. In a six-week repeat-dose toxicity study in rats, intravenous administration of fam-trastuzumab deruxtecan-nxki resulted in incisor tooth toxicity including single cell necrosis in the base area (e.g., ameloblasts, odontoblasts) and degeneration of the enamel at ≥60 mg/kg (approximately ≥9 times the human recommended dose of 5.4 mg/kg based on AUC), abnormal formation or hypoplasia of the dentin, hemorrhage in the sub-enamel organ tissue, and focal lack of the cementum at 197 mg/kg (approximately 19 times the human recommended dose of 5.4 mg/kg based on AUC). Degeneration of the enamel organ, abnormal dentin formation, hemorrhage in the sub-enamel organ tissue, focal lack of the cementum, and root fracture were observed at 197 mg/kg following a 9-week recovery period.

8.5 Geriatric Use

ENHERTU as Monotherapy

Of the 2355 patients with HER2-positive, HER2-low, or HER2-ultralow breast cancer treated with ENHERTU 5.4 mg/kg, 23% were 65 years or older and 5% were 75 years or older. No overall differences in efficacy within clinical studies were observed between patients ≥65 years of age compared to younger patients. There was a higher incidence of Grade 3-4 adverse reactions observed in patients aged 65 years or older (55%) as compared to younger patients (50%).

Of the 101 patients with HER2-mutant unresectable or metastatic NSCLC treated with ENHERTU 5.4 mg/kg, 40% were 65 years or older and 8% were 75 years or older. No overall differences in efficacy or safety were observed between patients ≥65 years of age compared to younger patients.

Of the 125 patients with HER2-positive locally advanced or metastatic gastric or GEJ adenocarcinoma treated with ENHERTU 6.4 mg/kg in DESTINY-Gastric01, 56% were 65 years or older and 14% were 75 years or older. No overall differences in efficacy or safety were observed between patients ≥65 years of age compared to younger patients.

Of the 192 patients with HER2-positive (IHC 3+) unresectable or metastatic solid tumors treated with ENHERTU 5.4 mg/kg in DESTINY-PanTumor02, DESTINY-Lung01 or DESTINY-CRC02, 39% were 65 years or older and 9% were 75 years or older. No overall differences in efficacy or safety were observed between patients ≥65 years of age compared to younger patients.

ENHERTU in Combination with Pertuzumab

In patients with HER2-positive unresectable or metastatic breast cancer treated with ENHERTU 5.4 mg/kg in combination with pertuzumab (N=431), 17% were 65 years or older and 3% were 75 years or older. No overall differences in efficacy or safety were observed between patients ≥65 years of age compared to younger patients.

8.6 Renal Impairment

No dose adjustment of ENHERTU is required in patients with mild (creatinine clearance [CLcr] ≥60 and <90 mL/min) or moderate (CLcr ≥30 and <60 mL/min) renal impairment [see Clinical Pharmacology (12.3)]. A higher incidence of Grade 1 and 2 ILD/pneumonitis has been observed in patients with moderate renal impairment [see Warnings and Precautions (5.1)]. Monitor patients with moderate renal impairment more frequently. The recommended dosage of ENHERTU has not been established for patients with severe renal impairment (CLcr <30 mL/min) [see Clinical Pharmacology (12.3)].

8.7 Hepatic Impairment

No dose adjustment of ENHERTU is required in patients with mild (total bilirubin ≤ULN and any AST >ULN or total bilirubin >1 to 1.5 times ULN and any AST) or moderate (total bilirubin >1.5 to 3 times ULN and any AST) hepatic impairment. In patients with moderate hepatic impairment, due to potentially increased exposure, closely monitor for increased toxicities related to the topoisomerase inhibitor, DXd [see Dosage and Administration (2.3)]. The recommended dosage of ENHERTU has not been established for patients with severe hepatic impairment (total bilirubin >3 times ULN and any AST) [see Clinical Pharmacology (12.3)].

11 DESCRIPTION

Fam-trastuzumab deruxtecan-nxki is a HER2-directed antibody and topoisomerase inhibitor conjugate. Fam-trastuzumab deruxtecan-nxki is an antibody-drug conjugate (ADC) composed of three components: 1) a humanized anti-HER2 IgG1 monoclonal antibody (mAb), covalently linked to 2) a topoisomerase inhibitor, via 3) a tetrapeptide-based cleavable linker. Deruxtecan is composed of a protease-cleavable maleimide tetrapeptide linker and the topoisomerase inhibitor, DXd, which is an exatecan derivative.

The antibody is produced in Chinese hamster ovary cells by recombinant DNA technology, and the topoisomerase inhibitor and linker are produced by chemical synthesis. Approximately 8 molecules of deruxtecan are attached to each antibody molecule. Fam-trastuzumab deruxtecan-nxki has the following structure:

ENHERTU (fam-trastuzumab deruxtecan-nxki) is a sterile, white to yellowish white, preservative-free lyophilized powder in single-dose vials. Each vial delivers 100 mg of fam-trastuzumab deruxtecan-nxki, L-histidine (4.45 mg), L-histidine hydrochloride monohydrate (20.2 mg), polysorbate 80 (1.5 mg), and sucrose (450 mg). Following reconstitution with 5 mL of Sterile Water for Injection, USP, the resulting concentration of fam-trastuzumab deruxtecan-nxki is 20 mg/mL with a pH of 5.5. The resulting solution is administered by intravenous infusion following dilution.

12 CLINICAL PHARMACOLOGY

12.1 Mechanism of Action

Fam-trastuzumab deruxtecan-nxki is a HER2-directed antibody-drug conjugate. The antibody is a humanized anti-HER2 IgG1. The small molecule, DXd, is a topoisomerase I inhibitor attached to the antibody by a cleavable linker. Following binding to HER2 on tumor cells, fam-trastuzumab deruxtecan-nxki undergoes internalization and intracellular linker cleavage by lysosomal enzymes. Upon release, the membrane-permeable DXd causes DNA damage and apoptotic cell death.

12.2 Pharmacodynamics

Exposure-Response Relationships

Exposure relationship for efficacy has not been fully characterized. Higher systemic exposure to fam-trastuzumab deruxtecan-nxki was associated with a higher incidence rate of any grade ILD.

Cardiac Electrophysiology

The administration of multiple doses of ENHERTU 6.4 mg/kg every 3 weeks did not show a large mean effect (i.e., >20 ms) on the QTc interval in an open-label, single-arm study in 51 patients with metastatic HER2-positive cancer.

12.3 Pharmacokinetics

The pharmacokinetics of fam-trastuzumab deruxtecan-nxki was evaluated in patients with cancer. Following a single dose, exposures (Cmax and AUC) of fam-trastuzumab deruxtecan-nxki and released topoisomerase inhibitor (DXd) increased proportionally over a dose range of 3.2 mg/kg to 8 mg/kg (approximately 0.6 to 1.5 times the recommended dose in breast cancer, NSCLC, and HER2-positive (IHC 3+) solid tumors and 0.5 to 1.25 times the recommended dose in gastric cancer).

At the recommended dosage of ENHERTU for patients with metastatic breast cancer, NSCLC, and HER2-positive (IHC 3+) solid tumors, the geometric mean (coefficient of variation [CV]%) Cmax of fam-trastuzumab deruxtecan-nxki and DXd were 132 µg/mL (20%) and 4.7 ng/mL (48%), respectively, and the AUC of fam-trastuzumab deruxtecan-nxki and DXd were 772 µg∙day/mL (27%) and 29 ng∙day/mL (48%), respectively. Accumulation of fam-trastuzumab deruxtecan-nxki was approximately 35% at steady-state (Cycle 3).

At the recommended dosage of ENHERTU for patients with HER2-positive gastric cancer, the geometric mean Cmax,ss of fam-trastuzumab deruxtecan-nxki and DXd were 126 µg/mL (18%) and 5.2 ng/mL (42%), respectively, and the AUCss of fam-trastuzumab deruxtecan-nxki and DXd were 743 µg∙day/mL (26%) and 33 ng∙day/mL (43%), respectively. Accumulation of fam-trastuzumab deruxtecan-nxki was approximately 39% at steady-state (Cycle 3).

Distribution

The estimated volume of distribution of the central compartment (Vc) of fam-trastuzumab deruxtecan-nxki was 2.68 L.

DXd plasma protein binding is approximately 97% and the blood-to-plasma ratio is approximately 0.6, in vitro.

Elimination

The median elimination half-life (t1/2) of fam-trastuzumab deruxtecan-nxki is 5.4-5.7 days. The estimated systemic clearance of fam-trastuzumab deruxtecan-nxki was 0.41 L/day.

The median elimination half-life (t1/2) of DXd is 5.4-6.1 days. The estimated systemic clearance of DXd was 18.3 L/h.

Metabolism

The humanized HER2 IgG1 monoclonal antibody is expected to be degraded into small peptides and amino acids via catabolic pathways in the same manner as endogenous IgG.

In vitro, DXd is primarily metabolized by CYP3A4.

Specific Populations

No clinically significant differences in the pharmacokinetics of fam-trastuzumab deruxtecan-nxki or DXd were observed for age (20-96 years); race (Asian vs Non-Asian), including White, and Black or African American; sex; body weight (27.3-125.4 kg); tumor types; mild hepatic impairment; mild or moderate renal impairment.

The pharmacokinetics of fam-trastuzumab deruxtecan-nxki or DXd in patients with moderate to severe hepatic impairment or severe renal impairment is unknown.

Drug Interaction Studies

Clinical Studies

Effect of CYP3A Inhibitors on DXd: Coadministration of itraconazole, a strong CYP3A inhibitor, with multiple doses of ENHERTU increased steady state AUC0-17 days of fam-trastuzumab deruxtecan-nxki by 11% and DXd by 18%. The impact of these changes is not clinically meaningful.

Effect of OATP Inhibitors on DXd: Coadministration of ritonavir, a dual inhibitor of OATP1B/CYP3A, with multiple doses of ENHERTU increased steady state AUC0-17 days of fam-trastuzumab deruxtecan-nxki by 19% and DXd by 22%. The impact of these changes is not clinically meaningful.

In Vitro Studies

Effects of DXd on CYP Enzymes: DXd does not inhibit CYP1A2, CYP2B6, CYP2C8, CYP2C9, CYP2C19, CYP2D6, and CYP3A nor induce CYP1A2, CYP2B6, or CYP3A.

Effects of DXd on Transporters: At clinically relevant concentrations (steady-state Cmax of ~0.2 μmol/L), DXd has a low potential to inhibit OAT1 (IC50 value of 12.7 μmol/L), OAT3, OCT1, OCT2, OATP1B1 (IC50 value of 14.4 μmol/L), OATP1B3, MATE1, MATE2-K, P-gp, BCRP, or BSEP transporters.

Effects of Other Drugs on DXd: DXd is a substrate of OATP1B1, OATP1B3, MATE2-K, P-gp, MRP1, and BCRP.

12.6 Immunogenicity

The observed incidence of anti-drug antibodies (ADA) is highly dependent on the sensitivity and specificity of the assay. Differences in assay methods preclude meaningful comparisons of the incidence of ADA in the studies described below with the incidence of ADA in other studies, including those of fam-trastuzumab deruxtecan-nxki or of other fam-trastuzumab deruxtecan products.

Among patients who received ENHERTU as a single agent over a 6 to 9 month treatment period in 13 clinical trials, anti-fam-trastuzumab deruxtecan-nxki antibodies developed in 2.2% (49/2,231) of patients who received ENHERTU 5.4 mg/kg every three weeks and in 2.6% (21/793) of patients who received ENHERTU 6.4 mg/kg every three weeks. Among patients who received ENHERTU (5.4 mg/kg every three weeks) in combination with pertuzumab for a median of 16 months in 2 clinical trials, anti-fam-trastuzumab deruxtecan-nxki antibodies developed in 7.7% (33/426) of patients.

These anti-drug antibodies have no clinically significant effect on the pharmacokinetics or safety of fam-trastuzumab deruxtecan-nxki. Because of the low occurrence of anti-drug antibodies, the effect of antibodies on the effectiveness of fam-trastuzumab deruxtecan-nxki products is unknown.

Among patients with anti-drug antibodies, neutralizing antibodies against fam-trastuzumab deruxtecan-nxki were detected in 6% (4/70) of patients who received ENHERTU as a single agent (5.4 mg/kg or 6.4 mg/kg every 3 weeks) and in 18% (6/33) of patients who received ENHERTU (5.4 mg/kg every 3 weeks) in combination with pertuzumab.

13 NONCLINICAL TOXICOLOGY

13.1 Carcinogenesis, Mutagenesis, Impairment of Fertility

Carcinogenicity studies have not been conducted with fam-trastuzumab deruxtecan-nxki.

The topoisomerase inhibitor component of fam-trastuzumab deruxtecan-nxki, DXd, was clastogenic in both an in vivo rat bone marrow micronucleus assay and an in vitro Chinese hamster lung chromosome aberration assay and was not mutagenic in an in vitro bacterial reverse mutation assay.

Fertility studies have not been conducted with fam-trastuzumab deruxtecan-nxki. In a six-week repeat-dose toxicity study in rats, intravenous administration of fam-trastuzumab deruxtecan-nxki resulted in spermatid retention at 20 mg/kg and 60 mg/kg (approximately 4 and 9 times the human recommended dose of 5.4 mg/kg based on AUC, respectively). Decreased testes and epididymides weights, tubular atrophy/degeneration in testes, and reduced sperm count in epididymides were observed at a dose of 197 mg/kg (19 times the human recommended dose of 5.4 mg/kg based on AUC). In a three-month repeat-dose toxicity study in monkeys, intravenous administration of fam-trastuzumab deruxtecan-nxki resulted in decreased numbers of round spermatids in the testes at seminiferous tubule stages V to VI at ≥30 mg/kg (≥7 times the human recommended dose of 5.4 mg/kg based on AUC). Evidence of reversibility was observed in monkeys by the end of a three-month recovery period.

14 CLINICAL STUDIES

14.1 HER2-Positive Metastatic Breast Cancer

DESTINY-Breast09

The efficacy of ENHERTU in combination with pertuzumab was evaluated in DESTINY-Breast09 (NCT04784715), a randomized, three-arm, multicenter, global study that enrolled 1157 adult patients with HER2-positive advanced, or metastatic breast cancer who had not received prior chemotherapy or HER2-targeted therapy or had received neoadjuvant or adjuvant HER2-targeted therapy more than 6 months before the diagnosis of advanced or metastatic disease. A single line of prior endocrine therapy was permitted for advanced or metastatic breast cancer. HER2 expression was confirmed at a central laboratory using PATHWAY anti-HER-2/neu (4B5) Rabbit Monoclonal Primary Antibody and HER2 Dual ISH DNA Probe Cocktail with HER2 positivity defined as HER2 IHC 3+ or ISH positive.

Patients were excluded for a history of ILD/pneumonitis requiring treatment with steroids or ILD/pneumonitis at screening, patients with symptomatic brain metastases, or ECOG performance status >1, and patients with a history of clinically significant cardiac disease.

Patients were randomized 1:1:1 to receive either, ENHERTU 5.4 mg/kg plus pertuzumab (N=383), THP (taxane [docetaxel or paclitaxel], trastuzumab, and pertuzumab) (N=387), or an investigational therapy (N=387) by intravenous infusion every 3 weeks until unacceptable toxicity or disease progression. Patients with hormone receptor (HR) positive disease (N=416) were allowed to receive concurrent endocrine therapy after 6 cycles of ENHERTU or after discontinuation of the taxane in the THP arm; this occurred in 13.5% of patients in the ENHERTU in the combination with pertuzumab arm and in 38.3% of patients in the THP arm. Randomization was stratified by prior treatment status (de novo vs recurrent), hormone receptor status, and PIK3CA mutation status.

The major efficacy outcome was progression-free survival (PFS) as assessed by blinded independent central review (BICR) based on Response Evaluation Criteria in Solid Tumors v1.1. Additional efficacy outcome measures were overall survival (OS) and confirmed objective response rate (ORR) assessed by BICR.

The median age was 54 years (range: 20-88); 82% were <65 years; 100% were female; 50% of the patients were Asian, 37% were White, 2% were American Indian or Alaska Native, and 3% were Black or African American; 14% were Hispanic or Latino; 8% other or race unknown; 52% had de novo disease and 48% had recurrent disease; 53% were HR-positive and 47% HR-negative; and 31% of patients had a PIK3CA mutation.

The trial demonstrated a statistically significant improvement in PFS for patients randomized to ENHERTU in combination with pertuzumab compared to THP. Efficacy results are summarized in Table 22 and Figure 1. At the time of the PFS analysis, OS data was not mature with 126 (16%) of patients who died across both study arms in the overall population.

Table 22: Efficacy Results in DESTINY-Breast09
Efficacy Parameter | ENHERTU 5.4 mg/kg + Pertuzumab N = 383 | THP [THP = taxane (docetaxel or paclitaxel), trastuzumab,and pertuzumab] N = 387
Progression-Free Survival (PFS) per BICR
Number of events (%) | 118 (31) | 172 (44)
Median, months (95% CI) | 40.7 (36.5, NE) | 26.9 (21.8, NE)
Hazard ratio (95% CI) | 0.56 (0.44, 0.71)
p-value [The stratified log-rank test p-value is compared with the allocated alpha of 0.00043 for this interim analysis (with 73% of the planned number of events for final analysis).] | < 0.00001
Confirmed Objective Response Rate (ORR) per BICR
Patients with Measurable Disease at Baseline, N | 374 | 371
ORR (95% CI) [95% CI was based on Clopper-Pearson method.] | 87 (83, 90) | 81 (77, 85)
Complete Response, % | 15 | 8
Partial Response, % | 72 | 73
CI = confidence interval; NE = not estimable, N = number

Figure 1: Kaplan-Meier Plot of Progression-Free Survival per BICR

DESTINY-Breast03

The efficacy of ENHERTU was evaluated in study DESTINY-Breast03 (NCT03529110), a multicenter, open-label, randomized trial that enrolled 524 patients with HER2-positive, unresectable and/or metastatic breast cancer who received prior trastuzumab and taxane therapy for metastatic disease or developed disease recurrence during or within 6 months of completing adjuvant therapy. HER2 expression was based on archival tissue tested at a central laboratory prior to enrollment with HER2 positivity defined as HER2 IHC 3+ or ISH positive. Patients were excluded for a history of ILD/pneumonitis requiring treatment with steroids, ILD/pneumonitis at screening, or clinically significant cardiac disease. Patients were also excluded for untreated and symptomatic brain metastases, ECOG performance status >1, or prior treatment with an anti-HER2 antibody-drug conjugate in the metastatic setting.

Patients were randomized 1:1 to receive either ENHERTU 5.4 mg/kg (N=261) or ado-trastuzumab emtansine 3.6 mg/kg (N=263) by intravenous infusion every 3 weeks until unacceptable toxicity or disease progression. Randomization was stratified by hormone receptor status, prior treatment with pertuzumab, and visceral versus non-visceral disease. Tumor imaging was obtained every 6 weeks and CT/MRI of the brain was mandatory for all patients at baseline. The major efficacy outcomes were progression-free survival (PFS) as assessed by blinded independent central review (BICR) based on Response Evaluation Criteria in Solid Tumors (RECIST) v.1.1 and overall survival (OS). Confirmed objective response rate (ORR) was an additional outcome measure.

The median age was 54 years (range: 20-83); 80% were <65 years; 99.6% were female; 60% were Asian, 27% were White, and 3.6% were Black; 11% of patients were of Hispanic/Latino ethnicity. Patients had an ECOG performance status of 0 (63%) or 1 (37%) at baseline. Seventy-three percent had visceral disease, 16% had brain metastases at baseline, 52% were hormone receptor positive (HR+), and 48% of patients had received one line of prior systemic therapy in the metastatic setting. The percentage of patients who had not received prior treatment for metastatic disease was 10%.

Efficacy results are summarized in Table 23 and Figures 2 and 3.

Table 23: Efficacy Results in DESTINY-Breast03
Efficacy Parameter | ENHERTU 5.4 mg/kg | Ado-trastuzumab emtansine 3.6 mg/kg
Progression-Free Survival (PFS) per BICR
N | 261 | 263
Number of events (%) | 87 (33.3) | 158 (60.1)
Median, months (95% CI) | NR (18.5, NE) | 6.8 (5.6, 8.2)
Hazard ratio (95% CI) | 0.28 (0.22, 0.37)
p-value [The stratified log-rank test p-value is compared with the allocated alpha of 0.0002 for this interim analysis (with 73% of the planned number of events for final analysis).] | p< 0.0001
Overall Survival (OS)
N | 261 | 263
Number of events (%) | 72 (27.6) | 97 (36.9)
Median, months (95% CI) | NR (40.5, NE) | NR (34.0, NE)
Hazard ratio (95% CI) | 0.64 (0.47, 0.87)
p-value [The stratified log-rank test p-value is compared with the allocated alpha of 0.013 for this interim analysis (with 68% of the planned number of events for final analysis).] | p=0.0037
Confirmed Objective Response Rate (ORR) per BICR [Analysis was performed based on the patients with measurable disease assessed by BICR at baseline.]
N | 248 | 241
n (%) | 205 (82.7) | 87 (36.1)
95% CI | (77.4, 87.2) | (30.0, 42.5)
Complete Response n (%) | 39 (15.7) | 20 (8.3)
Partial Response n (%) | 166 (66.9) | 67 (27.8)
CI = confidence interval; NR = not reached; NE = not estimable

Figure 2: Kaplan-Meier Plot of Progression-Free Survival per BICR (Intent-to-Treat Analysis Set)

Figure 3: Kaplan-Meier Plot of Overall Survival

DESTINY-Breast02

The efficacy of ENHERTU was evaluated in study DESTINY-Breast02 (NCT03523585), a multicenter, open-label, randomized study that enrolled 608 patients with HER2-positive, unresectable and/or metastatic breast cancer who were previously treated with ado-trastuzumab emtansine. HER2 expression was based on archival tissue tested at a central laboratory prior to enrollment with HER2 positivity defined as HER2 IHC 3+ or ISH positive. Patients were randomized 2:1 to receive either ENHERTU 5.4 mg/kg (N=406) by intravenous infusion every 3 weeks or treatment of physician's choice (TPC) (N=202, trastuzumab plus capecitabine or lapatinib plus capecitabine) until unacceptable toxicity or disease progression. Randomization was stratified by hormone receptor status, prior treatment with pertuzumab, and visceral versus non-visceral disease. The major efficacy outcomes were PFS as assessed by BICR based on RECIST v1.1 and OS.

The median age was 54 years (range: 22 to 88); 80% were <65 years; 99% were female; 63% were White, 29% were Asian, and 3% were Black or African American; 11% of patients were of Hispanic/Latino ethnicity. Patients had an ECOG performance status of 0 (57%) or 1 (42%) at baseline. Seventy-eight percent had visceral disease, 18% had brain metastases at baseline, 59% were hormone receptor positive (HR+), and 5% of patients had received one line of prior systemic therapy in the metastatic setting.

Efficacy results are summarized in Table 24 and Figures 4 and 5.

Table 24: Efficacy Results in DESTINY-Breast02
Efficacy Parameter | ENHERTU N=406 | Treatment of Physician's Choice N=202
PFS per BICR
Number of events (%) | 200 (49.3) | 125 (61.9)
Median, months (95% CI) | 17.8 (14.3, 20.8) | 6.9 (5.5, 8.4)
Hazard ratio (95% CI) | 0.36 (0.28, 0.45)
p-value | p<0.0001
Overall Survival (OS)
Number of events (%) | 143 (35.2) | 86 (42.6)
Median, months (95% CI) | 39.2 (32.7, NE) | 26.5 (21.0, NE)
Hazard ratio (95% CI) | 0.66 (0.50, 0.86)
p-value [The stratified log-rank test p-value is compared with the allocated alpha of 0.004 for this interim analysis (with 53% of the planned number of events for final analysis)] | p=0.0021
Confirmed Objective Response Rate (ORR) per BICR
n (%) | 283 (69.7) | 59 (29.2)
95% CI | (65.0, 74.1) | (23.0, 36.0)
Complete Response n (%) | 57 (14.0) | 10 (5.0)
Partial Response n (%) | 226 (55.7) | 49 (24.3)
Duration of Response per BICR
Median, months (95% CI) | 19.6 (15.9, NE) | 8.3 (5.8, 9.5)
CI = confidence interval; NE=not estimable

Figure 4: Kaplan-Meier Plot of Progression-free Survival Per BICR

Figure 5: Kaplan-Meier Plot of Overall Survival

DESTINY-Breast01

The efficacy of ENHERTU was evaluated in study DESTINY-Breast01 (NCT03248492), a multicenter, single-arm, trial that enrolled 184 female patients with HER2-positive, unresectable and/or metastatic breast cancer who had received two or more prior anti-HER2 therapies. Patients were excluded for a history of treated ILD or current ILD at screening. Patients were also excluded for history of clinically significant cardiac disease, active brain metastases, and ECOG performance status >1. HER2 expression was based on archival tissue tested at a central laboratory prior to enrollment with HER2 positivity defined as HER2 IHC 3+ or ISH positive.

Patients received ENHERTU 5.4 mg/kg by intravenous infusion every 3 weeks until unacceptable toxicity or disease progression. Tumor imaging was obtained every 6 weeks and CT/MRI of the brain was mandatory for patients with brain metastases at baseline. The major efficacy outcomes were confirmed objective response rate (ORR) assessed by independent central review (ICR) using RECIST v1.1 and duration of response (DOR).

The median age was 55 years (range: 28-96); 76% of patients were <65 years. All 184 patients were female, and the majority were White (55%) or Asian (38%). Patients had an ECOG performance status of 0 (55%) or 1 (44%) at baseline. Ninety-two percent had visceral disease, 29% had bone metastases, and 13% had brain metastases. Fifty-three percent were HR+. Sum of diameters of target lesions were <5 cm in 42%, and ≥5 cm in 50% (not evaluable by central review in 8% of patients).

The median number of prior cancer regimens in the locally advanced/metastatic setting was 5 (range: 2-17). All patients received prior trastuzumab, ado-trastuzumab emtansine, and 66% had prior pertuzumab.

Efficacy results are summarized in Table 25.

Table 25: Efficacy Results by Independent Central Review in DESTINY-Breast01
Efficacy Parameter | DESTINY-Breast01 N=184
Confirmed Objective Response Rate (95% CI) | 60.3% (52.9, 67.4)
Complete Response | 4.3%
Partial Response | 56.0%
Duration of Response [DOR is based on median duration of follow-up of 11.1 months.] Median, months (95% CI) [Median DOR based on Kaplan-Meier estimate; 95% CI calculated using Brookmeyer-Crowley method.] | 14.8 (13.8, 16.9)
ORR 95% CI calculated using Clopper-Pearson method.

14.2 HER2-Low and HER2-Ultralow Metastatic Breast Cancer

DESTINY-Breast06

The efficacy of ENHERTU was evaluated in study DESTINY-Breast06 (NCT04494425), a randomized (1:1), multicenter, open-label study that randomized 866 adult patients with advanced or metastatic HR+ breast cancer with HER2-low (IHC 1+ or IHC 2+/ISH-) or HER2-ultralow (IHC 0 with membrane staining) expression as determined by Ventana's PATHWAY anti-HER-2/neu (4B5) Rabbit Monoclonal Primary Antibody assay and evaluated at a central laboratory. HER2-ultralow is defined as membrane staining that is seen in >0 and ≤10% of tumor cells. Patients were eligible if they had disease progression on (a) at least 2 lines of endocrine therapy in the metastatic setting or (b) one line of endocrine therapy in the metastatic setting and demonstrated progression within 24 months of the start of adjuvant endocrine therapy, or within 6 months of starting first line endocrine therapy in combination with a CDK 4/6 inhibitor in the metastatic setting. Patients with prior chemotherapy in the neoadjuvant or adjuvant setting were eligible if they had a disease-free interval greater than 12 months. The study excluded patients with prior chemotherapy for advanced or metastatic disease, patients with a history of ILD/pneumonitis requiring treatment with steroids or ILD/pneumonitis at screening, uncontrolled or significant cardiovascular disease, untreated and symptomatic brain metastases, or ECOG performance status >1.

Patients were randomized to receive either ENHERTU 5.4 mg/kg (N=436) by intravenous infusion every three weeks or physician's choice of single agent chemotherapy (N=430, capecitabine 60%, nab-paclitaxel 24%, or paclitaxel 16%). Randomization was stratified by prior CDK4/6 inhibitor use (yes or no), prior taxane use in the non-metastatic setting (yes or no), and HER2 IHC status of tumor samples (IHC 2+/ISH- vs IHC 1+ vs IHC 0 with membrane staining). Treatment with ENHERTU was administered until disease progression, death, withdrawal of consent, or unacceptable toxicity.

The major efficacy outcome measure was PFS in patients with HER2-low breast cancer assessed by BICR based on RECIST v1.1. Additional efficacy outcome measures were PFS assessed by BICR based on RECIST v1.1 in the overall population, OS in HER2-low patients, and OS in the overall population.

The median age was 57 years (range: 28 to 87); 31% were age 65 or older; 99.9% were female; 53% were White, 35% were Asian, 0.8% were Black or African American, 0.1% were American Indian or Alaska Native, and 7% were of Hispanic/Latino ethnicity. Patients had an ECOG performance status of 0 (59%) or 1 (39%) at baseline; 18% were IHC 0 with membrane staining, 55% were IHC 1+, 27% were IHC 2+/ISH-; 67% had liver metastases, 32% had lung metastases, 8% had brain metastases, and 3% had bone-only metastases. Patients had a median of 2 prior lines of endocrine therapy in the metastatic setting (range: 1 to 5) with 17% having 1 and 68% having 2. Eighty-nine percent of patients had prior endocrine therapy in combination with CDK4/6i treatment in the metastatic setting, 41% had prior taxane use in the non-metastatic setting.

Efficacy results are summarized in Table 26 and Figure 6. At the time of the PFS final analysis, overall survival (OS) data was immature, and a total of 335 (39%) of patients had died across both study arms in the overall population.

Table 26: Efficacy Results in DESTINY-Breast06
Efficacy Parameter | HER2-low |  | Overall Population (HER2-low and HER2-ultralow)
Efficacy Parameter | ENHERTU (N=359) | Chemotherapy (N=354) | ENHERTU (N=436) | Chemotherapy (N=430)
Progression Free Survival (PFS) per BICR
Number of events (%) | 225 (62.7) | 232 (65.5) | 269 (61.7) | 271 (63.0)
Median, months (95% CI) | 13.2 (11.4, 15.2) | 8.1 (7.0, 9.0) | 13.2 (12.0, 15.2) | 8.1 (7.0, 9.0)
Hazard ratio (95% CI) | 0.62 (0.52, 0.75) [Based on stratified analysis with stratification factors prior CDK4/6 inhibitor use (yes vs no) and HER2 IHC status of tumor samples (IHC 1+ vs IHC 2+/ISH-).] |  | 0.64 (0.54, 0.76) [Based on unstratified analysis.]
p-value | <0.0001 |  | <0.0001
Confirmed Objective Response Rate (ORR) per BICR [Analysis was performed based on the patients with measurable disease assessed by BICR at baseline.]
N | 326 | 324 | 393 | 389
n (%) | 202 (62.0) | 114 (35.2) | 246 (62.6) | 134 (34.4)
95% CI | 56.5, 67.3 | 30.0, 40.7 | 57.6, 67.4 | 29.7, 39.4
Complete Response n (%) | 9 (2.8) | 0 | 10 (2.5) | 0
Partial Response n (%) | 193 (59.2) | 114 (35.2) | 236 (60.1) | 134 (34.4)
Duration of Response (DOR) per BICR
Median, months (95% CI) | 14.1 (11.9, 15.9) | 8.6 (6.7, 11.3) | 14.3 (12.5, 15.9) | 8.6 (6.9, 11.5)
CI = confidence interval

In an exploratory analysis of the HER2-ultralow subgroup (n=153), median PFS was 15.1 months (95% CI: 10.0, 17.3) in patients randomized to ENHERTU and 8.3 months (95% CI: 5.8, 15.2) in patients randomized to chemotherapy with a hazard ratio of 0.76 (95% CI: 0.49, 1.17). Confirmed ORR (BICR) was 65.7% (95% CI: 53.1, 76.8) and 30.8% (95% CI: 19.9, 43.4) in patients randomized to ENHERTU and chemotherapy and with measurable disease at baseline, respectively. Median DOR was 14.3 months (95% CI: 11.8, not estimable) and 14.1 months (95% CI: 5.9, not estimable) in patients randomized to ENHERTU and chemotherapy, respectively.

Figure 6: Kaplan-Meier Plot of Progression Free Survival (Overall Population)

DESTINY-Breast04

The efficacy of ENHERTU was evaluated in study DESTINY-Breast04 (NCT03734029), a randomized, multicenter, open-label study that enrolled 557 adult patients with unresectable or metastatic HER2-low breast cancer. The study included 2 cohorts: 494 hormone receptor-positive (HR+) patients and 63 hormone receptor-negative (HR-) patients. HER2-low expression was defined as IHC 1+ or IHC 2+/ISH-, as determined at a central laboratory using Ventana's PATHWAY anti-HER-2/neu (4B5) Rabbit Monoclonal Primary Antibody assay. Patients must have received chemotherapy in the metastatic setting or have developed disease recurrence during or within 6 months of completing adjuvant chemotherapy. Patients who were HR+ must have received at least one endocrine therapy or be ineligible for endocrine therapy. Patients were randomized 2:1 to receive either ENHERTU 5.4 mg/kg (N=373) by intravenous infusion every 3 weeks or physician's choice of chemotherapy (N=184, eribulin, capecitabine, gemcitabine, nab paclitaxel, or paclitaxel). Randomization was stratified by HER2 IHC status of tumor samples (IHC 1+ or IHC 2+/ISH-), number of prior lines of chemotherapy in the metastatic setting (1 or 2), and HR status/prior CDK4/6i treatment (HR+ with prior CDK4/6 inhibitor treatment, HR+ without prior CDK4/6 inhibitor treatment, or HR-). Treatment was administered until disease progression, death, withdrawal of consent, or unacceptable toxicity. The study excluded patients with a history of ILD/pneumonitis requiring treatment with steroids or ILD/pneumonitis at screening and clinically significant cardiac disease. Patients were also excluded for untreated or symptomatic brain metastases or ECOG performance status >1.

The major efficacy outcome measure was PFS in patients with HR+ breast cancer assessed by BICR based on RECIST v1.1. Additional efficacy outcome measures were PFS assessed by BICR based on RECIST v1.1 in the overall population (all randomized HR+ and HR- patients), OS in HR+ patients, and OS in the overall population.

The median age was 57 years (range: 28 to 81); 24% were age 65 or older; 99.6% were female; 48% were White, 40% were Asian, and 2% were Black or African American; 3.8% of patients were of Hispanic/Latino ethnicity. Patients had an ECOG performance status of 0 (55%) or 1 (45%) at baseline; 58% were IHC 1+, 42% were IHC 2+/ISH-; 70% had liver metastases, 33% had lung metastases, and 6% had brain metastases. In the metastatic setting, patients had a median of 3 prior lines of systemic therapy (range: 1 to 9) with 58% having 1 and 41% having 2 prior chemotherapy regimens; 3.9% were early progressors (progression in the neo/adjuvant setting). In HR+ patients, the median number of prior lines of endocrine therapy was 2 (range: 0 to 9) and 70% had prior CDK4/6i treatment.

Efficacy results are summarized in Table 27 and Figures 7 and 8.

Table 27: Efficacy Results in DESTINY-Breast04
Efficacy Parameter | HR+ Cohort |  | Overall Population (HR+ and HR- Cohorts)
Efficacy Parameter | ENHERTU (N=331) | Chemotherapy (N=163) | ENHERTU (N=373) | Chemotherapy (N=184)
Overall Survival
Number of events (%) | 126 (38.1) | 73 (44.8) | 149 (39.9) | 90 (48.9)
Median, months (95% CI) | 23.9 (20.8, 24.8) | 17.5 (15.2, 22.4) | 23.4 (20.0, 24.8) | 16.8 (14.5, 20.0)
Hazard ratio (95% CI) | 0.64 (0.48, 0.86) |  | 0.64 (0.49, 0.84)
p-value | 0.0028 |  | 0.001
Progression-Free Survival per BICR
Number of events (%) | 211 (63.7) | 110 (67.5) | 243 (65.1) | 127 (69.0)
Median, months (95% CI) | 10.1 (9.5, 11.5) | 5.4 (4.4, 7.1) | 9.9 (9.0, 11.3) | 5.1 (4.2, 6.8)
Hazard ratio (95% CI) | 0.51 (0.40, 0.64) |  | 0.50 (0.40, 0.63)
p-value | <0.0001 |  | <0.0001
Confirmed Objective Response Rate per BICR
n (%) | 175 (52.9) | 27 (16.6) | 195 (52.3) | 30 (16.3)
95% CI | 47.3, 58.4 | 11.2, 23.2 | 47.1, 57.4 | 11.3, 22.5
Complete Response n (%) | 12 (3.6) | 1 (0.6) | 13 (3.5) | 2 (1.1)
Partial Response n (%) | 164 (49.5) | 26 (16.0) | 183 (49.1) | 28 (15.2)
Duration of Response per BICR
Median, months (95% CI) | 10.7 (8.5, 13.7) | 6.8 (6.5, 9.9) | 10.7 (8.5, 13.2) | 6.8 (6.0, 9.9)
CI = confidence interval

Figure 7: Kaplan-Meier Plot of Overall Survival (Overall Population)

Figure 8: Kaplan-Meier Plot of Progression-Free Survival (Overall Population)

14.3 HER2-Mutant Unresectable or Metastatic Non-Small Cell Lung Cancer

ENHERTU was evaluated in DESTINY-Lung01 (NCT03505710) and at two dose levels in DESTINY-Lung02 (NCT04644237). Patients were prospectively selected for treatment with ENHERTU based on the presence of activating HER2 (ERBB2) mutations by local testing using tissue. Samples from DESTINY-Lung01 were retrospectively tested using Oncomine™ Dx Target Test (Life Technologies Corporation, Tissue-test) and Guardant360® CDx test (Guardant Health Inc., Plasma test). Demographic and baseline disease characteristics were similar for patients in DESTINY-Lung01 and DESTINY-Lung02, except for race (34% Asian vs 79% Asian, respectively). Response rates were consistent across dose levels. Increased rates of ILD/pneumonitis were observed at the higher dose. The approved recommended dose of 5.4 mg/kg intravenously every 3 weeks in the DESTINY-Lung02 study is described below [see Adverse Reactions (6.1)].

The efficacy of ENHERTU was evaluated in DESTINY-Lung02, a multicenter, multicohort, randomized, blinded, dose-optimization trial. Eligible patients were required to have unresectable or metastatic HER2-mutant non-squamous NSCLC with disease progression after one prior systemic therapy. Patients with a history of steroid dependent ILD/pneumonitis, clinically significant cardiac disease, clinically active brain metastases, and ECOG performance status >1 were excluded. Patients received ENHERTU 5.4 mg/kg by intravenous infusion every 3 weeks until disease progression or unacceptable toxicity. Tumor imaging was obtained every 6 weeks and CT/MRI of the brain was mandatory for patients with stable brain metastases at baseline.

Results from an interim efficacy analysis in a pre-specified patient cohort are described below. The major efficacy outcomes were confirmed ORR as assessed by BICR using RECIST v1.1 and DOR.

The median age was 58 years (range 30 to 78); 69% were female; 79% were Asian, 12% were White, and 10% were other races; 29% had an ECOG performance status of 0 and 71% had 1; 33% had stable brain metastases; 94% had a mutation in the ERBB2 kinase domain and 6% had a mutation in the extracellular domain. The median number of prior regimens was 2 (range: 1 to 12); 100% of patients received prior platinum therapy, 71% received prior immunotherapy, and 44% received both in combination. Fifty percent of patients were never-smokers and 50% were former smokers; 96% of patients had adenocarcinoma histology.

Efficacy results are provided in Table 28.

Table 28: Efficacy Results for DESTINY-Lung02 [Data cut-off: 22 June 2022]
Efficacy Parameter | DESTINY-Lung02 N=52
Confirmed Objective Response Rate (95% CI) | 57.7% (43.2, 71.3)
Complete Response | 1.9%
Partial Response | 55.8%
Duration of Response Median, months (95% CI) [Median DOR based on Kaplan-Meier estimate; 95% CI calculated using Brookmeyer-Crowley method] | 8.7 (7.1, NE)
ORR 95% CI calculated using Clopper-Pearson method
NE=not estimable

14.4 HER2-Positive Locally Advanced or Metastatic Gastric Cancer

The efficacy of ENHERTU was evaluated in study DESTINY-Gastric01 (NCT03329690), a multicenter, open-label, randomized trial conducted in Japan and South Korea that enrolled 188 adult patients with HER2-positive (IHC 3+ or IHC 2+/ISH positive), locally advanced or metastatic gastric or GEJ adenocarcinoma who had progressed on at least two prior regimens including trastuzumab, a fluoropyrimidine- and a platinum-containing chemotherapy. HER2 expression was determined by a central lab on tissue obtained either before or after prior trastuzumab treatment. Patients were excluded for a history of treated or current ILD, a history of clinically significant cardiac disease, active brain metastases, or ECOG performance status >1.

Patients were randomized 2:1 to receive ENHERTU (N=126) 6.4 mg/kg intravenously every 3 weeks or physician's choice of chemotherapy: irinotecan monotherapy (N=55) 150 mg/m^2 intravenously every 2 weeks or paclitaxel monotherapy (N=7) 80 mg/m^2 intravenously weekly. Randomization was stratified by HER2 status (IHC 3+ or IHC 2+/ISH+), ECOG performance status (0 or 1), and region (Japan or South Korea). Tumor imaging assessments were performed at screening and every 6 weeks from the first treatment dose. Treatment was administered until unacceptable toxicity or disease progression. The major efficacy outcomes were ORR assessed by ICR according to RECIST v1.1 and OS in the intent-to-treat population. Additional efficacy outcomes were PFS and DOR.

The median age was 66 years (range 28 to 82); 76% were male; and 100% were Asian. All patients received a trastuzumab product. Patients had an ECOG performance status of either 0 (49%) or 1 (51%); 87% had gastric adenocarcinoma and 13% had GEJ adenocarcinoma; 76% were IHC 3+ and 23% were IHC 2+/ISH+; 65% had inoperable advanced cancer; 35% had postoperative recurrent cancer; 54% had liver metastases; 29% had lung metastases; 45% had three or more prior regimens in the locally advanced or metastatic setting. A total of 30% of patients were identified as HER2-positive using tissue obtained following prior treatment with a trastuzumab product.

Efficacy results are summarized in Table 29, and the Kaplan-Meier curve for OS is shown in Figure 9.

Table 29: Efficacy Results in DESTINY-Gastric01
Efficacy Parameter | ENHERTU N=126 | Irinotecan or Paclitaxel N=62
Overall Survival (OS) [OS was evaluated following a statistically significant outcome of ORR.]
Median, months (95% CI) [Median based on Kaplan-Meier estimate; 95% CI for median calculated using Brookmeyer-Crowley method] | 12.5 (9.6, 14.3) | 8.4 (6.9,10.7)
Hazard ratio (95% CI) [Based on the stratified Cox proportional hazards regression model (stratified by region)] | 0.59 (0.39, 0.88)
p-value [Based on the stratified log-rank test (stratified by region)] | 0.0097
Progression-Free Survival (PFS) [Assessed by independent central review]
Median, months (95% CI) | 5.6 (4.3, 6.9) | 3.5 (2.0, 4.3)
Hazard ratio (95% CI) | 0.47 (0.31, 0.71)
Confirmed Objective Response Rate (ORR)
n (%) | 51 (40.5) | 7 (11.3)
95% CI [95% exact binomial confidence interval] | (31.8, 49.6) | (4.7, 21.9)
p-value [Based on the stratified Cochran-Mantel-Haenszel test (stratified by region)] | <0.0001
Complete Response n (%) | 10 (7.9) | 0 (0.0)
Partial Response n (%) | 41 (32.5) | 7 (11.3)
Duration of Response (DOR)
Median, months (95% CI) | 11.3 (5.6, NR) | 3.9 (3.0, 4.9)
CI = confidence interval; NR = not reached

Figure 9: Kaplan-Meier Plot of Overall Survival

14.5 HER2-Positive (IHC 3+) Unresectable or Metastatic Solid Tumors

The efficacy of ENHERTU was evaluated in 192 adult patients with previously treated unresectable or metastatic HER2-positive (IHC 3+) solid tumors who were enrolled in one of three multicenter trials: DESTINY-PanTumor02, DESTINY-Lung01, and DESTINY-CRC02. All three studies excluded patients with a history of ILD/pneumonitis requiring treatment with steroids or ILD/pneumonitis at screening and clinically significant cardiac disease. Patients were also excluded for active brain metastases or ECOG performance status >1. Patients received ENHERTU 5.4 mg/kg by intravenous infusion every three weeks. Treatment was administered until disease progression, death, withdrawal of consent, or unacceptable toxicity. The major efficacy outcome measure in all three of the studies was confirmed objective response rate (ORR) and an additional efficacy outcome measure was duration of response (DOR). All outcomes were assessed by independent central review (ICR) based on RECIST v1.1.

DESTINY-PanTumor02

DESTINY-PanTumor02 (NCT04482309) was a multicenter, multicohort, open-label trial that included 111 adult patients with locally advanced, unresectable, or metastatic HER2-positive (IHC 3+ by either local or central assessment) solid tumors that progressed following at least one prior systemic regimen in the advanced/metastatic setting or that had no satisfactory alternative treatment option.

The median age was 64 years (range 23 to 85); 59% were female; 58% were White, 34% were Asian, and 4% were Black or African American; 3% of patients were of Hispanic/Latino ethnicity. Patients had an ECOG performance status of either 0 (49%) or 1 (51%) at baseline. The median number of prior regimens in any treatment setting was 2.

DESTINY-Lung01

DESTINY-Lung01 (NCT03505710) was a multicenter, open-label, 2-cohort trial that included 17 patients with previously treated, unresectable, or metastatic, centrally confirmed HER2-positive (IHC 3+) NSCLC. Patients must have relapsed from or be refractory to standard treatment or have no available standard treatment.

The median age was 59 years (range 31 to 74); 59% were male; 65% were White, 18% were Asian, and 12% were Black or African American. Patients had an ECOG performance status of either 0 (12%) or 1 (88%) at baseline. The median number of prior regimens in any treatment setting was 3.

DESTINY-CRC02

DESTINY-CRC02 (NCT04744831) was a multicenter, randomized, 2-arm trial that included 64 patients with previously treated, unresectable or metastatic centrally confirmed HER2-positive (IHC 3+) colorectal cancer (CRC). Unless contraindicated, patients must have received fluoropyrimidine, oxaliplatin and irinotecan. If clinically indicated, patients must have received anti-EGFR treatment, anti-VEGF treatment and anti-PDL1 therapy.

The median age was 58 years (range 25 to 78); 53% were male; 55% were Asian and 41% were White; 1.6% of patients were of Hispanic/Latino ethnicity. Patients had an ECOG performance status of either 0 (58%) or 1 (42%) at baseline. The median number of prior regimens in any treatment setting was 4.

Efficacy results are summarized in Table 30 and Table 31.

Table 30: Efficacy Results in HER2-Positive (IHC 3+) Patients in DESTINY-PanTumor02, DESTINY-Lung01, and DESTINY-CRC02
Efficacy Parameter | DESTINY-PanTumor02 N=111 | DESTINY-Lung01 N=17 | DESTINY-CRC02 N=64
Confirmed ORR (95% CI) [Assessed by independent central review] [CI is derived based on the Clopper-Pearson method] | 51.4% (41.7, 61.0) | 52.9% (27.8, 77.0) | 46.9% (34.3, 59.8)
Complete Response Rate | 2.7% | 5.9% | 0%
Partial Response Rate | 48.6% | 47.1% | 46.9%
Duration of Response
Median [Calculated using the Kaplan-Meier technique] , months (range) | 19.4 (1.3, 27.9+) | 6.9 (4.0, 11.7+) | 5.5 (1.3+, 9.7+)
CI=Confidence interval
+ Denotes ongoing response

Table 31: Efficacy Results in HER2-positive (IHC 3+) Patients by Tumor Type in DESTINY-PanTumor02, DESTINY-Lung01, and DESTINY-CRC02
Tumor Type | Patients | Confirmed ORR [Assessed by independent central review] | DOR Range
 | N | % (95% CI) [CI is derived based on the Clopper-Pearson method] | (months)
Colorectal Cancer | 64 | 46.9 (34.3, 59.8) | (1.3+, 9.7+)
Bladder Cancer | 27 | 37.0 (19.4, 57.6) | (2.8, 19.7+)
Biliary Tract Cancer | 22 | 45.5 (24.4, 67.8) | (2.1, 22.0+)
NSCLC | 17 | 52.9 (27.8, 77.0) | (4.0, 11.7+)
Endometrial Cancer | 16 | 56.3 (29.9, 80.2) | (5.8, 23.7+)
Ovarian Cancer | 15 | 66.7 (38.4, 88.2) | (1.3, 27.9+)
Cervical Cancer | 10 | 70.0 (34.8, 93.3) | (7.2+, 25.0+)
Salivary Gland Cancer | 9 | 66.7 (29.9,92.5) | (5.6, 20.1)
Pancreatic Cancer | 5 | 0 (0, 52.2) | NA
Oropharyngeal Neoplasm | 1 | PR | 15.3
Vulvar Cancer | 1 | PR | 2.6
Extramammary Paget's Disease | 1 | PR | 19.4
Lacrimal Gland Cancer | 1 | PR | 19.8+
Lip and/or Oral Cavity Cancer | 1 | SD | NA
Esophageal Adenocarcinoma | 1 | PR | 2.8
Esophageal Squamous Cell Carcinoma | 1 | PD | NA
CI=Confidence interval, NA=Not applicable, PD=Progressive disease, PR=Partial response, SD=Stable disease
+ Denotes ongoing response

15 REFERENCES

1. OSHA Hazardous Drugs. OSHA. http://www.osha.gov/SLTC/hazardousdrugs/index.html

16 HOW SUPPLIED/STORAGE AND HANDLING

How Supplied/Storage

ENHERTU (fam-trastuzumab deruxtecan-nxki) for injection is a white to yellowish white lyophilized powder supplied as:

Carton Contents | NDC
One 100 mg single-dose vial | NDC 65597-406-01

Store vials in a refrigerator at 2ºC to 8ºC (36ºF to 46ºF) in the original carton to protect from light until time of reconstitution. Do not freeze. Do not shake the reconstituted or diluted solution [see Dosage and Administration (2.4)].

Special Handling

ENHERTU (fam-trastuzumab deruxtecan-nxki) is a hazardous drug. Follow applicable special handling and disposal procedures.^1

17 PATIENT COUNSELING INFORMATION

Advise the patient to read the FDA-approved patient labeling (Medication Guide).

Interstitial Lung Disease

- Inform patients of the risks of severe or fatal ILD. Advise patients to contact their healthcare provider immediately for any of the following: cough, shortness of breath, fever, or other new or worsening respiratory symptoms [see Warnings and Precautions (5.1)].

Neutropenia

- Advise patients of the possibility of developing neutropenia and to immediately contact their healthcare provider should they develop a fever, particularly in association with any signs of infection [see Warnings and Precautions (5.2)].

Left Ventricular Dysfunction

- Advise patients to contact their healthcare provider immediately for any of the following: new onset or worsening shortness of breath, cough, fatigue, swelling of ankles/legs, palpitations, sudden weight gain, dizziness, loss of consciousness [see Warnings and Precautions (5.3)].

Embryo-Fetal Toxicity

- Inform female patients of the potential risk to a fetus. Advise female patients to contact their healthcare provider of a known or suspected pregnancy [see Warnings and Precautions (5.4), Use in Specific Populations (8.1)].
- Advise females of reproductive potential to use effective contraception during treatment with ENHERTU and for 7 months after the last dose [see Use in Specific Populations (8.3)].
- Advise male patients with female partners of reproductive potential to use effective contraception during treatment with ENHERTU and for 4 months after the last dose [see Use in Specific Populations (8.3)].

Lactation

- Advise women not to breastfeed during treatment and for 7 months after the last dose of ENHERTU [see Use in Specific Populations (8.2)].

Infertility

- Advise males of reproductive potential that ENHERTU may impair fertility [see Use in Specific Populations (8.3)].

Manufactured by:
Daiichi Sankyo, Inc., Basking Ridge, NJ 07920

U.S. License No. 2128

Marketed by:
Daiichi Sankyo, Inc., Basking Ridge, NJ 07920 and AstraZeneca Pharmaceuticals LP, Wilmington, DE 19850

ENHERTU® is a registered trademark of Daiichi Sankyo Company, Ltd.
© 2025 Daiichi Sankyo Co., Ltd.

USPI-ENH-C19.1+DB09-1225-r010

Medication Guide
ENHERTU® (en-HER-too)
(fam-trastuzumab deruxtecan-nxki) for injection

What is the most important information I should know about ENHERTU?
ENHERTU can cause serious side effects, including:

- Lung problems that may be severe, life-threatening or that may lead to death. If you develop lung problems your healthcare provider may treat you with corticosteroid medicines. Tell your healthcare provider right away if you get any of the following signs and symptoms:
  - cough
  - trouble breathing or shortness of breath
  - fever
  - other new or worsening breathing symptoms (such as chest tightness, wheezing)
- Low white blood cell count (neutropenia). Low white blood cell counts are common with ENHERTU and can sometimes be severe. Your healthcare provider will check your white blood cell counts before starting ENHERTU and before starting each dose. Tell your healthcare provider right away if you develop any signs or symptoms of an infection or have fever or chills during treatment with ENHERTU.
- Heart problems that may affect your heart's ability to pump blood. Your healthcare provider will check your heart function before starting treatment with ENHERTU. Tell your healthcare provider right away if you get any of the following signs and symptoms:

- new or worsening shortness of breath
- coughing
- feeling tired
- swelling of your ankles or legs

- irregular heartbeat
- sudden weight gain
- dizziness or feeling light-headed
- loss of consciousness

Your healthcare provider will check you for these side effects during your treatment with ENHERTU. Your healthcare provider may reduce your dose, delay treatment or completely stop treatment with ENHERTU if you have severe side effects.

- Harm to your unborn baby. Tell your healthcare provider right away if you become pregnant or think you might be pregnant during treatment with ENHERTU.
  - If you are able to become pregnant, your healthcare provider should do a pregnancy test before you start treatment with ENHERTU.
  - Females who are able to become pregnant should use effective birth control (contraception) during treatment with ENHERTU and for 7 months after the last dose.
  - Males who have female partners that are able to become pregnant should use effective birth control (contraception) during treatment with ENHERTU and for 4 months after the last dose.

See "What are the possible side effects of ENHERTU?" for more information about side effects.

What is ENHERTU?
ENHERTU is a prescription medicine used to treat adults who have:

- human epidermal growth factor receptor 2 (HER2)-positive breast cancer that cannot be removed by surgery or has spread to other parts of the body (metastatic) in combination with pertuzumab as your first treatment. Your healthcare provider will perform a test to make sure ENHERTU in combination with pertuzumab is right for you.
- HER2-positive breast cancer that cannot be removed by surgery or that has spread to other parts of the body (metastatic), and who have received a prior anti-HER2 breast cancer treatment for metastatic disease or have breast cancer that has come back during or within 6 months of completing treatment for their early-stage breast cancer.
- HER2-low breast cancer that cannot be removed by surgery or that has spread to other parts of the body (metastatic), and who have received a prior chemotherapy for metastatic disease, or whose disease has returned during or within 6 months of completing adjuvant chemotherapy (after surgery). Your healthcare provider will perform a test to make sure ENHERTU is right for you.
- Hormone receptor (HR)-positive, HER2-low or HR-positive, HER2-ultralow breast cancer that cannot be removed by surgery or that has spread to other parts of the body (metastatic), and who have received one or more endocrine treatments for metastatic disease. Your healthcare provider will perform a test to make sure ENHERTU is right for you.
- non-small cell lung cancer (NSCLC) that has a certain mutation in the HER2 gene and cannot be removed by surgery or has spread to other parts of your body (metastatic), and who have received a prior treatment. Your healthcare provider will perform a test to make sure ENHERTU is right for you.
- stomach cancer called gastric or gastroesophageal junction (GEJ) adenocarcinoma that is HER2 positive and has spread to areas near your stomach (locally advanced) or that has spread to other parts of your body (metastatic), and who have received a prior trastuzumab-based regimen.
- solid tumors that are HER2-positive (IHC 3+) and that cannot be removed by surgery or have spread to other parts of your body (metastatic), and who have received a prior treatment and have no other satisfactory treatment options. Your healthcare provider will perform a test to make sure ENHERTU is right for you.

It is not known if ENHERTU is safe and effective in children.

Before you receive ENHERTU, tell your healthcare provider about all of your medical conditions, including if you:

- have lung or breathing problems
- have signs or symptoms of an infection
- have or have had any heart problems
- are breastfeeding or plan to breastfeed. It is not known if ENHERTU passes into your breast milk. Do not breastfeed during treatment with ENHERTU and for 7 months after the last dose.

Tell your healthcare provider about all the medicines you take, including prescription and over-the-counter medicines, vitamins, and herbal supplements.

How will I receive ENHERTU?

- You will receive ENHERTU into your vein through an intravenous (IV) line by your healthcare provider.
- ENHERTU is given 1 time every three weeks (21-day treatment cycle).
- Your healthcare provider will decide how many treatments you need.
- Your healthcare provider will give you medicines before your infusion to help prevent nausea and vomiting.
- Your healthcare provider may slow down or temporarily stop your infusion of ENHERTU if you have an infusion-related reaction, or permanently stop ENHERTU if you have severe infusion reactions.
- If you miss a planned dose of ENHERTU, call your healthcare provider right away to schedule an appointment. Do not wait until the next planned treatment cycle.

What are the possible side effects of ENHERTU?
ENHERTU can cause serious side effects. See "What is the most important information I should know about ENHERTU?"
The most common side effects of ENHERTU, when used in people with metastatic breast cancer, HER2-mutant non-small cell lung cancer, and other HER2-positive solid tumors include:

- low white blood cell counts
- nausea
- low red blood cell counts
- feeling tired
- low platelet counts
- increased liver function tests
- vomiting

- hair loss
- constipation
- low levels of blood potassium
- decreased appetite
- diarrhea
- muscle or bone pain

The most common side effects of ENHERTU in combination with pertuzumab, when used in people with HER2-positive breast cancer include:

- low white blood cell counts
- low red blood cell counts
- nausea
- increased liver function tests
- diarrhea
- low platelet counts
- low levels of blood potassium
- feeling tired

- hair loss
- vomiting
- upper respiratory tract infection
- constipation
- decreased appetite
- weight loss
- COVID-19
- muscle or bone pain
- stomach pain

The most common side effects of ENHERTU, when used in people with HER2-positive gastric or GEJ adenocarcinoma, include:

- low red blood cell counts
- low white blood cell counts
- low platelet counts
- nausea
- decreased appetite
- increased liver function tests
- feeling tired

- diarrhea
- low levels of blood potassium
- vomiting
- constipation
- fever
- hair loss

ENHERTU may cause fertility problems in males, which may affect the ability to father children. Talk to your healthcare provider if you have concerns about fertility.
These are not all of the possible side effects of ENHERTU. Call your doctor for medical advice about side effects. You may report side effects to FDA at 1-800-FDA-1088.

General information about the safe and effective use of ENHERTU.
Medicines are sometimes prescribed for purposes other than those listed in a Medication Guide. You can ask your pharmacist or healthcare provider for information about ENHERTU that is written for healthcare professionals.

What are the ingredients in ENHERTU?
Active Ingredient: fam-trastuzumab deruxtecan-nxki.
Inactive Ingredients: L-histidine, L-histidine hydrochloride monohydrate, polysorbate 80, and sucrose.
Manufactured by: Daiichi Sankyo, Inc., Basking Ridge, NJ 07920
U.S. License No. 2128
Marketed by: Daiichi Sankyo, Inc., Basking Ridge, NJ 07920 and AstraZeneca Pharmaceuticals LP, Wilmington, DE 19850
ENHERTU® is a registered trademark of Daiichi Sankyo Company, Ltd.
© 2025 Daiichi Sankyo Co., Ltd.
USMG-ENH-C19.1+DB09-1225-r009
For more information, call 1-877-437-7763 or go to https://www.ENHERTU.com.

This Medication Guide has been approved by the U.S. Food and Drug Administration.

Revised: 12/2025

PRINCIPAL DISPLAY PANEL - 100 mg Vial Carton

NDC 65597-406-01
Rx only

ENHERTU®
(fam-trastuzumab deruxtecan-nxki)

For Injection

100 mg per vial

For Intravenous Infusion Only

Dispense the enclosed Medication Guide to each patient.
Reconstitute and Dilute prior to administration
Single-Dose Vial
Discard Unused Portion

Hazardous Drug

KEEP REFRIGERATED

1 vial

Daiichi-Sankyo
AstraZeneca